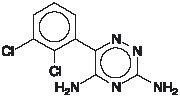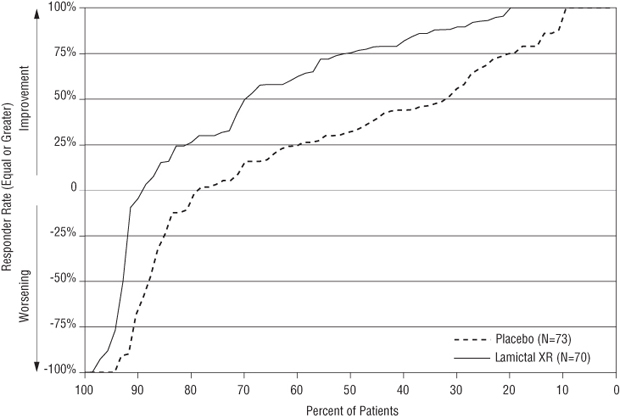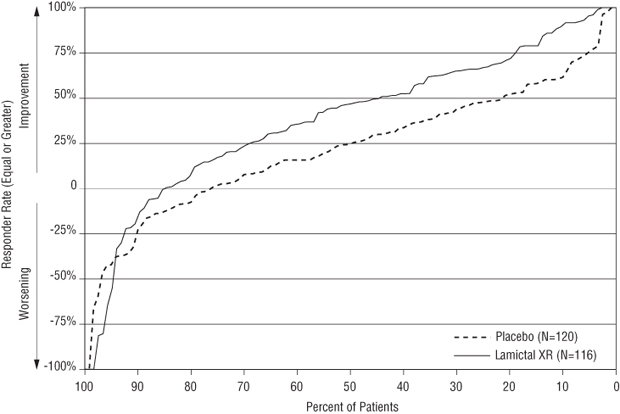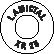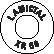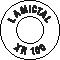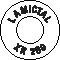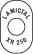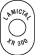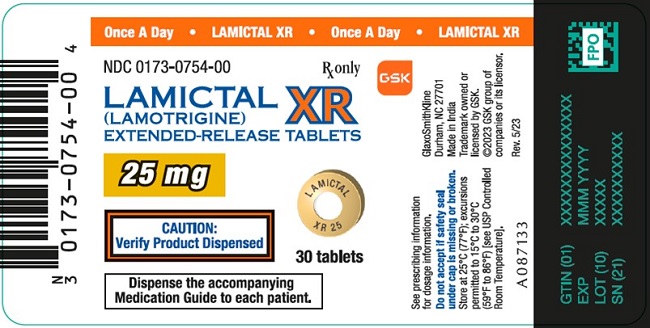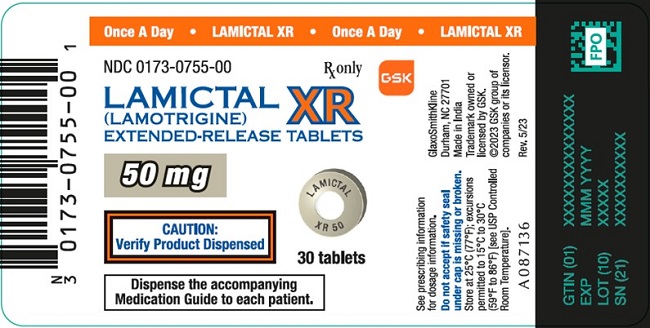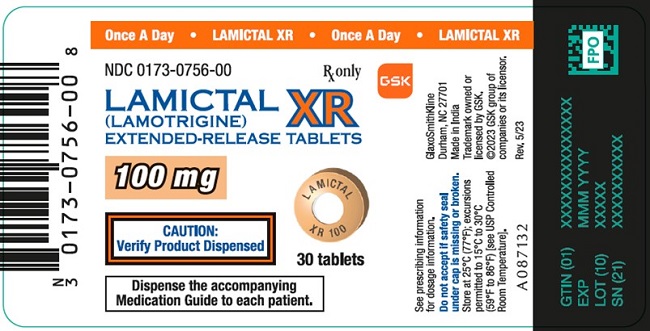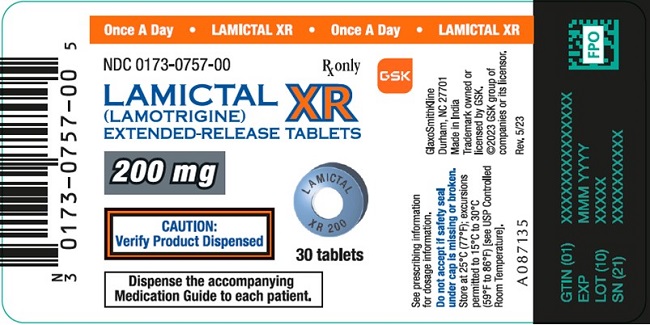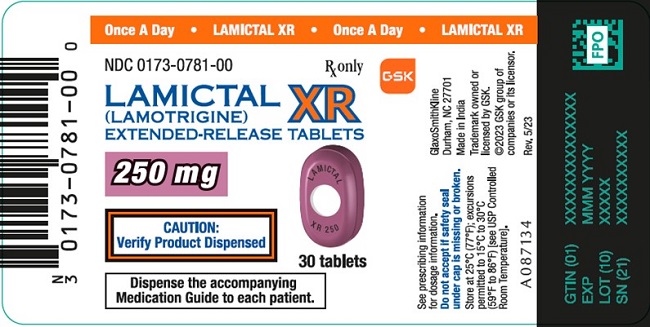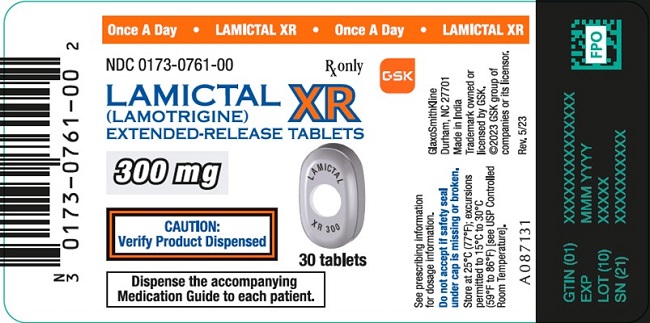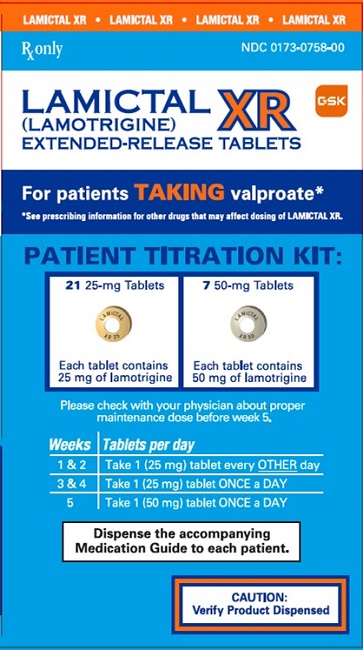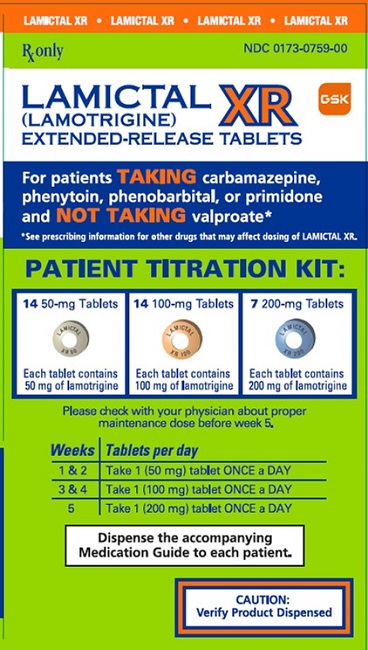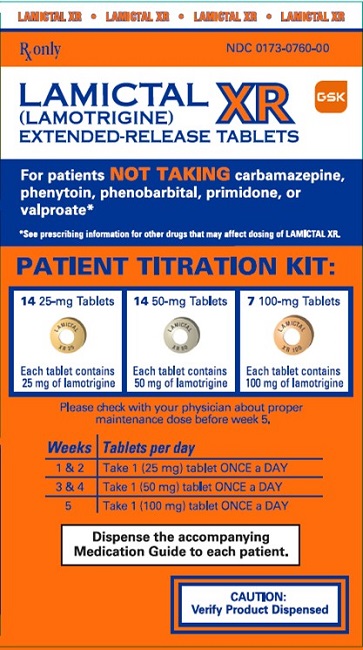 DRUG LABEL: LAMICTAL
NDC: 0173-0754 | Form: TABLET, FILM COATED, EXTENDED RELEASE
Manufacturer: GlaxoSmithKline LLC
Category: prescription | Type: HUMAN PRESCRIPTION DRUG LABEL
Date: 20251010

ACTIVE INGREDIENTS: LAMOTRIGINE 25 mg/1 1
INACTIVE INGREDIENTS: GLYCERYL MONOSTEARATE; HYPROMELLOSE, UNSPECIFIED; LACTOSE MONOHYDRATE; MAGNESIUM STEARATE; METHACRYLIC ACID; Polyethylene glycol 400; POLYSORBATE 80; TITANIUM DIOXIDE; TRIETHYL CITRATE; SILICON DIOXIDE; FERRIC OXIDE YELLOW

HIGHLIGHTS OF PRESCRIBING INFORMATION

These highlights do not include all the information needed to use LAMICTAL XR safely and effectively. See full prescribing information for LAMICTAL XR.
LAMICTAL XR (lamotrigine) extended-release tablets, for oral use
Initial U.S. Approval: 1994

RECENT MAJOR CHANGES

Boxed Warning
Dosage and Administration (2.1, 2.2)
Warnings and Precautions,
Serious Skin Rashes (5.1)
Concomitant Use with Estrogen-Containing Products, Including Oral Contraceptives (5.9)
Sudden Unexplained Death in Epilepsy (5.12) – removal

10/2025
4/2025
10/2025
4/2025
4/2025

WARNING: SERIOUS SKIN RASHES

See full prescribing information for complete boxed warning.

- Cases of life-threatening serious rashes, including Stevens-Johnson syndrome and toxic epidermal necrolysis, and/or rash-related death have been caused by lamotrigine. The rate of serious rash is greater in pediatric patients than in adults. Additional factors that may increase the risk of rash include:
  - coadministration with valproate.
  - exceeding recommended initial dose of LAMICTAL XR.
  - exceeding recommended dose escalation for LAMICTAL XR.
  - presence of the HLA-B*1502 allele. (5.1)
- Benign rashes are also caused by lamotrigine; however, it is not possible to predict which rashes will prove to be serious or life threatening. LAMICTAL XR should be discontinued at the first sign of rash, unless the rash is clearly not drug related. (5.1)

1 INDICATIONS AND USAGE

LAMICTAL XR is indicated for:

- adjunctive therapy for primary generalized tonic-clonic seizures (PGTC) and partial-onset seizures with or without secondary generalization in patients aged 13 years and older. (1.1)
- conversion to monotherapy in patients aged 13 years and older with partial-onset seizures who are receiving treatment with a single antiepileptic drug (AED). (1.2)

Limitation of use: Safety and effectiveness in patients younger than 13 years have not been established. (1.3)

2 DOSAGE AND ADMINISTRATION

- Do not exceed the recommended initial dosage and subsequent dose escalation. (2.1)
- Initiation of adjunctive therapy and conversion to monotherapy requires slow titration dependent on concomitant AEDs; the prescriber must refer to the appropriate algorithm in Dosage and Administration. (2.2, 2.3)
  - Adjunctive therapy: Target therapeutic dosage range is 200 to 600 mg daily and is dependent on concomitant AEDs. (2.2)
  - Conversion to monotherapy: Target therapeutic dosage range is 250 to 300 mg daily. (2.3)
- Conversion from immediate-release lamotrigine to LAMICTAL XR: The initial dose of LAMICTAL XR should match the total daily dose of the immediate-release lamotrigine. Patients should be closely monitored for seizure control after conversion. (2.4)
- Do not restart LAMICTAL XR in patients who discontinued due to rash unless the potential benefits clearly outweigh the risks. (2.1, 5.1)
- Adjustments to maintenance doses will be necessary in most patients starting or stopping estrogen-containing products, including oral contraceptives. (2.1, 5.9)
- Discontinuation: Taper over a period of at least 2 weeks (approximately 50% dose reduction per week). (2.1, 5.10)

3 DOSAGE FORMS AND STRENGTHS

Extended-release tablets: 25 mg, 50 mg, 100 mg, 200 mg, 250 mg, and 300 mg. (3.1, 16)

4 CONTRAINDICATIONS

Hypersensitivity to the drug or its ingredients. (Boxed Warning, 4)

5 WARNINGS AND PRECAUTIONS

- Life-threatening serious rash and/or rash-related death: Discontinue at the first sign of rash, unless the rash is clearly not drug related. (Boxed Warning, 5.1)
- Hemophagocytic lymphohistiocytosis: Consider this diagnosis and evaluate patients immediately if they develop signs or symptoms of systemic inflammation. Discontinue LAMICTAL XR if an alternative etiology is not established. (5.2)
- Fatal or life-threatening hypersensitivity reaction: Multiorgan hypersensitivity reactions, also known as drug reaction with eosinophilia and systemic symptoms (DRESS), may be fatal or life threatening. Early signs may include rash, fever, and lymphadenopathy. These reactions may be associated with other organ involvement, such as hepatitis, hepatic failure, blood dyscrasias, or acute multiorgan failure. LAMICTAL XR should be discontinued if alternate etiology for this reaction is not found. (5.3)
- Cardiac rhythm and conduction abnormalities: Based on in vitro findings, LAMICTAL XR could cause serious arrhythmias and/or death in patients with certain underlying cardiac disorders or arrhythmias. Any expected or observed benefit of LAMICTAL XR in an individual patient with clinically important structural or functional heart disease must be carefully weighed against the risk for serious arrythmias and/or death for that patient. (5.4)
- Blood dyscrasias (e.g., neutropenia, thrombocytopenia, pancytopenia): May occur, either with or without an associated hypersensitivity syndrome. Monitor for signs of anemia, unexpected infection, or bleeding. (5.5)
- Suicidal behavior and ideation: Monitor for suicidal thoughts or behaviors. (5.6)
- Aseptic meningitis: Monitor for signs of meningitis. (5.7)
- Medication errors due to product name confusion: Strongly advise patients to visually inspect tablets to verify the received drug is correct. (5.8, 16, 17)

6 ADVERSE REACTIONS

- Most common adverse reactions with use as adjunctive therapy (treatment difference between LAMICTAL XR and placebo ≥4%) were dizziness, tremor/intention tremor, vomiting, and diplopia. (6.1)
- Most common adverse reactions with use as monotherapy were similar to those seen with previous trials conducted with immediate-release lamotrigine and LAMICTAL XR. (6.1)

To report SUSPECTED ADVERSE REACTIONS, contact GlaxoSmithKline at 1-888-825-5249 or FDA at 1-800-FDA-1088 or www.fda.gov/medwatch.

7 DRUG INTERACTIONS

- Valproate increases lamotrigine concentrations more than 2-fold. (7, 12.3)
- Carbamazepine, phenytoin, phenobarbital, primidone, and rifampin decrease lamotrigine concentrations by approximately 40%. (7, 12.3)
- Estrogen-containing oral contraceptives decrease lamotrigine concentrations by approximately 50%. (7, 12.3)
- Protease inhibitors lopinavir/ritonavir and atazanavir/lopinavir decrease lamotrigine exposure by approximately 50% and 32%, respectively. (7, 12.3)
- Coadministration with organic cationic transporter 2 (OCT2) substrates with narrow therapeutic index is not recommended (7, 12.3)

8 USE IN SPECIFIC POPULATIONS

- Pregnancy: Based on animal data may cause fetal harm. (8.1)
- Hepatic impairment: Dosage adjustments required in patients with moderate and severe liver impairment. (2.1, 8.6)
- Renal impairment: Reduced maintenance doses may be effective for patients with significant renal impairment. (2.1, 8.7)

FULL PRESCRIBING INFORMATION

WARNING: SERIOUS SKIN RASHES

LAMICTAL XR can cause serious rashes requiring hospitalization and discontinuation of treatment. The incidence of these rashes, which have included Stevens-Johnson syndrome, is approximately 0.8% (8 per 1,000) in pediatric patients (aged 2 to 16 years) receiving immediate-release lamotrigine as adjunctive therapy for epilepsy and 0.3% (3 per 1,000) in adults on adjunctive therapy for epilepsy. In a prospectively followed cohort of 1,983 pediatric patients (aged 2 to 16 years) with epilepsy taking adjunctive immediate release lamotrigine, there was 1 rash-related death. LAMICTAL XR is not approved for patients younger than 13 years. In worldwide postmarketing experience, rare cases of toxic epidermal necrolysis and/or rash-related death have been reported in adult and pediatric patients, but their numbers are too few to permit a precise estimate of the rate.

The risk of serious rash caused by treatment with LAMICTAL XR is not expected to differ from that with immediate-release lamotrigine. However, the relatively limited treatment experience with LAMICTAL XR makes it difficult to characterize the frequency and risk of serious rashes caused by treatment with LAMICTAL XR.

In addition to age, factors that may increase the risk of occurrence or the severity of rash caused by LAMICTAL XR include (1) coadministration of LAMICTAL XR with valproate (includes valproic acid and divalproex sodium), (2) exceeding the recommended initial dose of LAMICTAL XR, (3) exceeding the recommended dose escalation for LAMICTAL XR. , or (4) the presence of the HLA-B*1502 allele. However, cases have occurred in the absence of these factors.

Nearly all cases of life-threatening rashes caused by immediate-release lamotrigine have occurred within 2 to 8 weeks of treatment initiation. However, isolated cases have occurred after prolonged treatment (e.g., 6 months). Accordingly, duration of therapy cannot be relied upon as means to predict the potential risk heralded by the first appearance of a rash.

Although benign rashes are also caused by LAMICTAL XR, it is not possible to predict reliably which rashes will prove to be serious or life threatening. Accordingly, LAMICTAL XR should ordinarily be discontinued at the first sign of rash, unless the rash is clearly not drug related. Discontinuation of treatment may not prevent a rash from becoming life threatening or permanently disabling or disfiguring [see Warnings and Precautions (5.1)].

1 INDICATIONS AND USAGE

1.1 Adjunctive Therapy

LAMICTAL XR is indicated as adjunctive therapy for primary generalized tonic-clonic (PGTC) seizures and partial-onset seizures with or without secondary generalization in patients aged 13 years and older.

1.2 Monotherapy

LAMICTAL XR is indicated for conversion to monotherapy in patients aged 13 years and older with partial-onset seizures who are receiving treatment with a single antiepileptic drug (AED).

Safety and effectiveness of LAMICTAL XR have not been established (1) as initial monotherapy or (2) for simultaneous conversion to monotherapy from 2 or more concomitant AEDs.

1.3 Limitation of Use

Safety and effectiveness of LAMICTAL XR for use in patients younger than 13 years have not been established.

2 DOSAGE AND ADMINISTRATION

LAMICTAL XR extended-release tablets are taken once daily, with or without food. Tablets must be swallowed whole and must not be chewed, crushed, or divided.

2.1 General Dosing Considerations

Rash

There are suggestions that the risk of severe, potentially life-threatening rash may be increased by (1) coadministration of LAMICTAL XR with valproate, (2) exceeding the recommended initial dose of lamictal XR, or (3) exceeding the recommended dose escalation for lamictal XR. However, cases have occurred in the absence of these factors [see Boxed Warning]. Therefore, it is important that the dosing recommendations be followed closely.

The risk of nonserious rash may be increased when the recommended initial dose and/or the rate of dose escalation for LAMICTAL XR is exceeded and in patients with a history of allergy or rash to other AEDs.

LAMICTAL XR Patient Titration Kits provide LAMICTAL XR at doses consistent with the recommended titration schedule for the first 5 weeks of treatment, based upon concomitant medications, for patients with partial-onset seizures and are intended to help reduce the potential for rash. The use of LAMICTAL XR Patient Titration Kits is recommended for appropriate patients who are starting or restarting LAMICTAL XR [see How Supplied/Storage and Handling (16)].

It is recommended that LAMICTAL XR not be restarted in patients who discontinued due to rash associated with prior treatment with lamotrigine unless the potential benefits clearly outweigh the risks. If the decision is made to restart a patient who has discontinued LAMICTAL XR, the need to restart with the initial dosing recommendations should be assessed. The greater the interval of time since the previous dose, the greater consideration should be given to restarting with the initial dosing recommendations. If a patient has discontinued lamotrigine for a period of more than 5 half-lives, it is recommended that initial dosing recommendations and guidelines be followed. The half-life of lamotrigine is affected by other concomitant medications [see Clinical Pharmacology (12.3)].

LAMICTAL XR Added to Drugs Known to Induce or Inhibit Glucuronidation

Because lamotrigine is metabolized predominantly by glucuronic acid conjugation, drugs that are known to induce or inhibit glucuronidation may affect the apparent clearance of lamotrigine. Drugs that induce glucuronidation include carbamazepine, phenytoin, phenobarbital, primidone, rifampin, estrogen-containing products, including oral contraceptives, and the protease inhibitors lopinavir/ritonavir and atazanavir/ritonavir. Valproate inhibits glucuronidation. For dosing considerations for LAMICTAL XR in patients on estrogen-containing products including contraceptives and atazanavir/ritonavir, see below and Table 5. For dosing considerations for LAMICTAL XR in patients on other drugs known to induce or inhibit glucuronidation, see Table 1 and Table 5.

Target Plasma Levels

A therapeutic plasma concentration range has not been established for lamotrigine. Dosing of LAMICTAL XR should be based on therapeutic response [see Clinical Pharmacology (12.3)].

Women Taking Estrogen-Containing Oral Contraceptives

Starting LAMICTAL XR in Women Taking Estrogen-Containing Oral Contraceptives: Although estrogen-containing oral contraceptives have been shown to increase the clearance of lamotrigine, no adjustments to the recommended dose-escalation guidelines for LAMICTAL XR should be necessary solely based on the use of estrogen‑containing oral contraceptives [see Clinical Pharmacology (12.3)]. Therefore, dose escalation should follow the recommended guidelines for initiating adjunctive therapy with LAMICTAL XR based on the concomitant AED or other concomitant medications (see Table 1). See below for adjustments to maintenance doses of LAMICTAL XR in women taking estrogen-containing oral contraceptives.

Adjustments to the Maintenance Dose of LAMICTAL XR in Women Taking Estrogen-Containing Oral Contraceptives:

(1) Taking Estrogen-Containing Oral Contraceptives: In women not taking carbamazepine, phenytoin, phenobarbital, primidone, or other drugs such as rifampin and the protease inhibitors lopinavir/ritonavir and atazanavir/ritonavir that induce lamotrigine glucuronidation, the maintenance dose of LAMICTAL XR will in most cases need to be increased by as much as 2-fold over the recommended target maintenance dose to maintain a consistent lamotrigine plasma level [see Drug Interactions (7), Clinical Pharmacology (12.3)].

(2) Starting Estrogen-Containing Oral Contraceptives: In women taking a stable dose of LAMICTAL XR and not taking carbamazepine, phenytoin, phenobarbital, primidone, or other drugs such as rifampin and the protease inhibitors lopinavir/ritonavir and atazanavir/ritonavir that induce lamotrigine glucuronidation, the maintenance dose will in most cases need to be increased by as much as 2-fold to maintain a consistent lamotrigine plasma level [see Drug Interactions (7), Clinical Pharmacology (12.3)]. The dose increases should begin at the same time that the oral contraceptive is introduced and continue, based on clinical response, no more rapidly than 50 to 100 mg/day every week. Dose increases should not exceed the recommended rate (see Table 1) unless lamotrigine plasma levels or clinical response support larger increases. Gradual transient increases in lamotrigine plasma levels may occur during the week of inactive hormonal preparation (pill-free week), and these increases will be greater if dose increases are made in the days before or during the week of inactive hormonal preparation. Increased lamotrigine plasma levels could result in additional adverse reactions, such as dizziness, ataxia, and diplopia. If adverse reactions attributable to LAMICTAL XR consistently occur during the pill-free week, dose adjustments to the overall maintenance dose may be necessary. Dose adjustments limited to the pill-free week are not recommended. For women taking LAMICTAL XR in addition to carbamazepine, phenytoin, phenobarbital, primidone, or other drugs such as rifampin and the protease inhibitors lopinavir/ritonavir and atazanavir/ritonavir that induce lamotrigine glucuronidation, no adjustment to the dose of LAMICTAL XR should be necessary [see Drug Interactions (7), Clinical Pharmacology (12.3)].

(3) Stopping Estrogen-Containing Oral Contraceptives: In women not taking carbamazepine, phenytoin, phenobarbital, primidone, or other drugs such as rifampin and the protease inhibitors lopinavir/ritonavir and atazanavir/ritonavir that induce lamotrigine glucuronidation, the maintenance dose of LAMICTAL XR will in most cases need to be decreased by as much as 50% in order to maintain a consistent lamotrigine plasma level [see Drug Interactions (7), Clinical Pharmacology (12.3)]. The decrease in dose of LAMICTAL XR should not exceed 25% of the total daily dose per week over a 2-week period, unless clinical response or lamotrigine plasma levels indicate otherwise [see Clinical Pharmacology (12.3)]. In women taking LAMICTAL XR in addition to carbamazepine, phenytoin, phenobarbital, primidone, or other drugs such as rifampin and the protease inhibitors lopinavir/ritonavir and atazanavir/ritonavir that induce lamotrigine glucuronidation, no adjustment to the dose of LAMICTAL XR should be necessary [see Drug Interactions (7), Clinical Pharmacology (12.3)].

Women and Other Hormonal Contraceptive Preparations or Hormone Replacement Therapy

The effect of other hormonal contraceptive preparations or hormone replacement therapy (HRT) on the pharmacokinetics of lamotrigine has not been systematically evaluated. Other estrogen-containing therapies, such as HRT, may interfere with lamotrigine. Therefore, close clinical monitoring on effectiveness of LAMICTAL XR with dose adjustment may be necessary [see Warnings and Precautions (5.9)]. It has been reported that ethinylestradiol, not progestogens, increased the clearance of lamotrigine up to 2-fold, and the progestin-only pills had no effect on lamotrigine plasma levels. Therefore, adjustments to the dosage of LAMICTAL XR in the presence of progestogens alone will likely not be needed.

Patients Taking Atazanavir/Ritonavir

While atazanavir/ritonavir does reduce the lamotrigine plasma concentration, no adjustments to the recommended dose-escalation guidelines for LAMICTAL XR should be necessary solely based on the use of atazanavir/ritonavir. Dose escalation should follow the recommended guidelines for initiating adjunctive therapy with LAMICTAL XR based on concomitant AED or other concomitant medications (see Tables 1 and 5). In patients already taking maintenance doses of LAMICTAL XR and not taking glucuronidation inducers, the dose of LAMICTAL XR may need to be increased if atazanavir/ritonavir is added or decreased if atazanavir/ritonavir is discontinued [see Clinical Pharmacology (12.3)].

Patients with Hepatic Impairment

Experience in patients with hepatic impairment is limited. Based on a clinical pharmacology study in 24 subjects with mild, moderate, and severe liver impairment, the following general recommendations can be made [see Use in Specific Populations (8.6), Clinical Pharmacology (12.3]. No dosage adjustment is needed in patients with mild liver impairment. Initial, escalation, and maintenance doses should generally be reduced by approximately 25% in patients with moderate and severe liver impairment without ascites and 50% in patients with severe liver impairment with ascites. Escalation and maintenance doses may be adjusted according to clinical response.

Patients with Renal Impairment

Initial doses of LAMICTAL XR should be based on patients’ concomitant medications (see Table 1); reduced maintenance doses may be effective for patients with significant renal impairment [see Use in Specific Populations (8.7), Clinical Pharmacology (12.3)]. Few patients with severe renal impairment have been evaluated during chronic treatment with immediate-release lamotrigine. Because there is inadequate experience in this population, LAMICTAL XR should be used with caution in these patients.

Discontinuation Strategy

For patients receiving LAMICTAL XR in combination with other AEDs, a re-evaluation of all AEDs in the regimen should be considered if a change in seizure control or an appearance or worsening of adverse reactions is observed.

If a decision is made to discontinue therapy with LAMICTAL XR, a step-wise reduction of dose over at least 2 weeks (approximately 50% per week) is recommended unless safety concerns require a more rapid withdrawal [see Warnings and Precautions (5.10)].

Discontinuing carbamazepine, phenytoin, phenobarbital, primidone, or other drugs such as rifampin and the protease inhibitors lopinavir/ritonavir and atazanavir/ritonavir that induce lamotrigine glucuronidation should prolong the half-life of lamotrigine; discontinuing valproate should shorten the half-life of lamotrigine.

2.2 Adjunctive Therapy for Primary Generalized Tonic-Clonic and Partial-Onset Seizures

This section provides specific dosing recommendations for patients aged 13 years and older. Specific dosing recommendations are provided depending upon concomitant AEDs or other concomitant medications.

Table 1. Escalation Regimen for LAMICTAL XR in Patients Aged 13 Years and Older
 | In Patients TAKING Valproatea | In Patients NOT TAKING Carbamazepine, Phenytoin, Phenobarbital, Primidone,b or Valproatea | In Patients TAKING Carbamazepine, Phenytoin, Phenobarbital, or Primidoneb and NOT TAKING Valproatea
Weeks 1 and 2 | 25 mg every other day | 25 mg every day | 50 mg every day
Weeks 3 and 4 | 25 mg every day | 50 mg every day | 100 mg every day
Week 5 | 50 mg every day | 100 mg every day | 200 mg every day
Week 6 | 100 mg every day | 150 mg every day | 300 mg every day
Week 7 | 150 mg every day | 200 mg every day | 400 mg every day
Maintenance range (Week 8 and onward) | 200 to 250 mg every dayc | 300 to 400 mg every dayc | 400 to 600 mg every dayc
a Valproate has been shown to inhibit glucuronidation and decrease the apparent clearance of lamotrigine [see Drug Interactions (7), Clinical Pharmacology (12.3)].
b Drugs that induce lamotrigine glucuronidation and increase clearance, other than the specified AEDs, include estrogen-containing oral contraceptives, rifampin, and the protease inhibitors lopinavir/ritonavir and atazanavir/ritonavir. Dosing recommendations for estrogen-containing products, including oral contraceptives, and the protease inhibitor atazanavir/ritonavir can be found in General Dosing Considerations [see Dosage and Administration (2.1)]. Patients on rifampin and the protease inhibitor lopinavir/ritonavir should follow the same dosing titration/maintenance regimen used with AEDs that induce glucuronidation and increase clearance [see Dosage and Administration (2.1), Drug Interactions (7), Clinical Pharmacology (12.3)].
c Dose increases at Week 8 or later should not exceed 100 mg daily at weekly intervals.

2.3 Conversion from Adjunctive Therapy to Monotherapy

The goal of the transition regimen is to attempt to maintain seizure control while mitigating the risk of serious rash associated with the rapid titration of LAMICTAL XR.

To avoid an increased risk of rash, the recommended maintenance dosage range of LAMICTAL XR as monotherapy is 250 to 300 mg given once daily.

The recommended initial dose and subsequent dose escalations for LAMICTAL XR should not be exceeded [see Boxed Warning].

Conversion from Adjunctive Therapy with Carbamazepine, Phenytoin, Phenobarbital, or Primidone to Monotherapy with LAMICTAL XR

After achieving a dose of 500 mg/day of LAMICTAL XR using the guidelines in Table 1, the concomitant enzyme-inducing AED should be withdrawn by 20% decrements each week over a 4-week period. Two weeks after completion of withdrawal of the enzyme-inducing AED, the dosage of LAMICTAL XR may be decreased no faster than 100 mg/day each week to achieve the monotherapy maintenance dosage range of 250 to 300 mg/day.

The regimen for the withdrawal of the concomitant AED is based on experience gained in the controlled monotherapy clinical trial using immediate-release lamotrigine.

Conversion from Adjunctive Therapy with Valproate to Monotherapy with LAMICTAL XR

The conversion regimen involves the 4 steps outlined in Table 2.

Table 2. Conversion from Adjunctive Therapy with Valproate to Monotherapy with LAMICTAL XR in Patients Aged 13 Years and Older with Epilepsy
 | LAMICTAL XR | Valproate
Step 1 | Achieve a dose of 150 mg/day according to guidelines in Table 1. | Maintain established stable dose.
Step 2 | Maintain at 150 mg/day. | Decrease dose by decrements no greater than 500 mg/day/week to 500 mg/day and then maintain for 1 week.
Step 3 | Increase to 200 mg/day. | Simultaneously decrease to 250 mg/day and maintain for 1 week.
Step 4 | Increase to 250 or 300 mg/day. | Discontinue.

Conversion from Adjunctive Therapy with Antiepileptic Drugs other than Carbamazepine, Phenytoin, Phenobarbital, Primidone, or Valproate to Monotherapy with LAMICTAL XR

After achieving a dosage of 250 to 300 mg/day of LAMICTAL XR using the guidelines in Table 1, the concomitant AED should be withdrawn by 20% decrements each week over a 4-week period. No adjustment to the monotherapy dose of LAMICTAL XR is needed.

2.4 Conversion from Immediate-Release Lamotrigine Tablets to LAMICTAL XR

Patients may be converted directly from immediate-release lamotrigine to LAMICTAL XR extended-release tablets. The initial dose of LAMICTAL XR should match the total daily dose of immediate-release lamotrigine. However, some subjects on concomitant enzyme-inducing agents may have lower plasma levels of lamotrigine on conversion and should be monitored [see Clinical Pharmacology (12.3)].

Following conversion to LAMICTAL XR, all patients (but especially those on drugs that induce lamotrigine glucuronidation) should be closely monitored for seizure control [see Drug Interactions (7)]. Depending on the therapeutic response after conversion, the total daily dose may need to be adjusted within the recommended dosing instructions (see Table 1).

3 DOSAGE FORMS AND STRENGTHS

3.1 Extended-Release Tablets

25-mg, yellow with white center, round, biconvex, film-coated tablets printed with “LAMICTAL” and “XR 25.”

50-mg, green with white center, round, biconvex, film-coated tablets printed with “LAMICTAL” and “XR 50.”

100-mg, orange with white center, round, biconvex, film-coated tablets printed with “LAMICTAL” and “XR 100.”

200-mg, blue with white center, round, biconvex, film-coated tablets printed with “LAMICTAL” and “XR 200.”

250-mg, purple with white center, caplet-shaped, film-coated tablets printed with “LAMICTAL” and “XR 250.”

300-mg, gray with white center, caplet-shaped, film-coated tablets printed with “LAMICTAL” and “XR 300.”

4 CONTRAINDICATIONS

LAMICTAL XR is contraindicated in patients who have demonstrated hypersensitivity (e.g., rash, angioedema, acute urticaria, extensive pruritus, mucosal ulceration) to the drug or its ingredients [see Boxed Warning, Warnings and Precautions (5.1, 5.3)].

5 WARNINGS AND PRECAUTIONS

5.1 Serious Skin Rashes [see Boxed Warning]

The risk of serious rash caused by treatment with LAMICTAL XR is not expected to differ from that with immediate-release lamotrigine [see Boxed Warning]. However, the relatively limited treatment experience with LAMICTAL XR makes it difficult to characterize the frequency and risk of serious rashes caused by treatment with LAMICTAL XR.

Pediatric Population

The incidence of serious rash associated with hospitalization and discontinuation of immediate-release lamotrigine in a prospectively followed cohort of pediatric patients (aged 2 to 16 years) with epilepsy receiving adjunctive therapy with immediate-release lamotrigine was approximately 0.8% (16 of 1,983). When 14 of these cases were reviewed by 3 expert dermatologists, there was considerable disagreement as to their proper classification. To illustrate, 1 dermatologist considered none of the cases to be Stevens-Johnson syndrome; another assigned 7 of the 14 to this diagnosis. There was 1 rash-related death in this 1,983-patient cohort. Additionally, there have been rare cases of toxic epidermal necrolysis with and without permanent sequelae and/or death in U.S. and foreign postmarketing experience.

There is evidence that the inclusion of valproate in a multidrug regimen increases the risk of serious, potentially life-threatening rash in pediatric patients. In pediatric patients who used valproate concomitantly, 1.2% (6 of 482) experienced a serious rash compared with 0.6% (6 of 952) patients not taking valproate.

LAMICTAL XR is not approved in patients younger than 13 years.

Adult Population

Serious rash associated with hospitalization and discontinuation of immediate-release lamotrigine occurred in 0.3% (11 of 3,348) of adult patients who received immediate-release lamotrigine in premarketing clinical trials of epilepsy. In worldwide postmarketing experience, rare cases of rash-related death have been reported, but their numbers are too few to permit a precise estimate of the rate.

Among the rashes leading to hospitalization were Stevens-Johnson syndrome, toxic epidermal necrolysis, angioedema, and those associated with multiorgan hypersensitivity [see Warnings and Precautions (5.3)].

Risk Factors

Concomitant Use of Valproate

There is evidence that the inclusion of valproate in a multidrug regimen increases the risk of serious, potentially life-threatening rash in adults. Specifically, of 584 patients administered immediate-release lamotrigine with valproate in epilepsy clinical trials, 6 (1%) were hospitalized in association with rash; in contrast, 4 (0.16%) of 2,398 clinical trial patients and volunteers administered immediate-release lamotrigine in the absence of valproate were hospitalized.

Patients with History of Allergy or Rash to Other Antiepileptic Drugs

The risk of rash may be increased in patients with a history of allergy or rash to other AEDs.

Not Adhering to the Recommended Dosage

The risk of rash is increased by both exceeding the recommended initial dose of LAMICTAL XR and exceeding the recommended dose escalation for LAMICTAL XR.

Patients with Genetic Variant Human Leukocyte Antigen (HLA)‑B*1502 Allele

Retrospective case-control studies in patients of certain Asian ancestry (e.g., Han Chinese and Thai) suggest that the HLA-B*1502 allele is associated with an increased risk (approximately 2‑3 times higher) of developing Stevens-Johnson syndrome (SJS)/toxic epidermal necrolysis (TEN) in patients using lamotrigine. The risks and benefits of therapy should be weighed when considering use of LAMICTAL XR in patients known to be positive for HLA-B*1502. Application of HLA genotyping as a screening tool has important limitations and must never substitute for appropriate clinical vigilance and patient management. Many HLA‑B*1502‑positive patients treated with LAMICTAL XR will not develop SJS/TEN or other hypersensitivity reactions, and these reactions can still occur in HLA‑B*1502‑negative patients of any ethnicity.

5.2 Hemophagocytic Lymphohistiocytosis

Hemophagocytic lymphohistiocytosis (HLH) has occurred in pediatric and adult patients taking LAMICTAL XR for various indications. HLH is a life-threatening syndrome of pathologic immune activation characterized by clinical signs and symptoms of extreme systemic inflammation. It is associated with high mortality rates if not recognized early and treated. Common findings include fever, hepatosplenomegaly, rash, lymphadenopathy, neurologic symptoms, cytopenias, high serum ferritin, hypertriglyceridemia, and liver function and coagulation abnormalities. In cases of HLH reported with LAMICTAL XR, patients have presented with signs of systemic inflammation (fever, rash, hepatosplenomegaly, and organ system dysfunction) and blood dyscrasias. Symptoms have been reported to occur within 8 to 24 days following the initiation of treatment. Patients who develop early manifestations of pathologic immune activation should be evaluated immediately, and a diagnosis of HLH should be considered. LAMICTAL XR should be discontinued if an alternative etiology for the signs or symptoms cannot be established.

5.3 Multiorgan Hypersensitivity Reactions and Organ Failure

Multiorgan hypersensitivity reactions, also known as drug reaction with eosinophilia and systemic symptoms (DRESS), have occurred with lamotrigine. Some have been fatal or life threatening. DRESS typically, although not exclusively, presents with fever, rash, and/or lymphadenopathy in association with other organ system involvement, such as hepatitis, nephritis, hematologic abnormalities, myocarditis, or myositis, sometimes resembling an acute viral infection. Eosinophilia is often present. This disorder is variable in its expression and other organ systems not noted here may be involved.

Fatalities associated with acute multiorgan failure and various degrees of hepatic failure have been reported in 2 of 3,796 adult patients and 4 of 2,435 pediatric patients who received lamotrigine in epilepsy clinical trials. Rare fatalities from multiorgan failure have also been reported in postmarketing use.

Isolated liver failure without rash or involvement of other organs has also been reported with lamotrigine.

It is important to note that early manifestations of hypersensitivity (e.g., fever, lymphadenopathy) may be present even though a rash is not evident. If such signs or symptoms are present, the patient should be evaluated immediately. LAMICTAL XR should be discontinued if an alternative etiology for the signs or symptoms cannot be established.

Prior to initiation of treatment with LAMICTAL XR, the patient should be instructed that a rash or other signs or symptoms of hypersensitivity (e.g., fever, lymphadenopathy) may herald a serious medical event and that the patient should report any such occurrence to a healthcare provider immediately.

5.4 Cardiac Rhythm and Conduction Abnormalities

In vitro testing showed that LAMICTAL XR exhibits Class IB antiarrhythmic activity at therapeutically relevant concentrations [see Clinical Pharmacology (12.2)]. Based on these in vitro findings, LAMICTAL XR could slow ventricular conduction (widen QRS) and induce proarrhythmia, which can lead to sudden death, in patients with clinically important structural or functional heart disease (i.e., patients with heart failure, valvular heart disease, congenital heart disease, conduction system disease, ventricular arrhythmias, cardiac channelopathies [e.g., Brugada syndrome], clinically important ischemic heart disease, or multiple risk factors for coronary artery disease). Any expected or observed benefit of LAMICTAL XR in an individual patient with clinically important structural or functional heart disease must be carefully weighed against the risks for serious arrythmias and/or death for that patient. Concomitant use of other sodium channel blockers may further increase the risk of proarrhythmia.

5.5 Blood Dyscrasias

There have been reports of blood dyscrasias with immediate-release lamotrigine that may or may not be associated with multiorgan hypersensitivity (also known as DRESS) [see Warnings and Precautions (5.3)]. These have included neutropenia, leukopenia, anemia, thrombocytopenia, pancytopenia, and, rarely, aplastic anemia and pure red cell aplasia.

5.6 Suicidal Behavior and Ideation

AEDs, including LAMICTAL XR, increase the risk of suicidal thoughts or behavior in patients taking these drugs for any indication. Patients treated with any AED for any indication should be monitored for the emergence or worsening of depression, suicidal thoughts or behavior, and/or any unusual changes in mood or behavior.

Pooled analyses of 199 placebo-controlled clinical trials (monotherapy and adjunctive therapy) of 11 different AEDs showed that patients randomized to 1 of the AEDs had approximately twice the risk (adjusted Relative Risk 1.8, 95% CI: 1.2, 2.7) of suicidal thinking or behavior compared with patients randomized to placebo. In these trials, which had a median treatment duration of 12 weeks, the estimated incidence of suicidal behavior or ideation among 27,863 AED-treated patients was 0.43%, compared with 0.24% among 16,029 placebo-treated patients, representing an increase of approximately 1 case of suicidal thinking or behavior for every 530 patients treated. There were 4 suicides in drug-treated patients in the trials and none in placebo-treated patients, but the number of events is too small to allow any conclusion about drug effect on suicide.

The increased risk of suicidal thoughts or behavior with AEDs was observed as early as 1 week after starting treatment with AEDs and persisted for the duration of treatment assessed. Because most trials included in the analysis did not extend beyond 24 weeks, the risk of suicidal thoughts or behavior beyond 24 weeks could not be assessed.

The risk of suicidal thoughts or behavior was generally consistent among drugs in the data analyzed. The finding of increased risk with AEDs of varying mechanism of action and across a range of indications suggests that the risk applies to all AEDs used for any indication. The risk did not vary substantially by age (5 to 100 years) in the clinical trials analyzed.

Table 3 shows absolute and relative risk by indication for all evaluated AEDs.

Table 3. Risk by Indication for Antiepileptic Drugs in the Pooled Analysis
Indication | Placebo Patients with Events per 1,000 Patients | Drug Patients with Events per 1,000 Patients | Relative Risk: Incidence of Events in Drug Patients/ Incidence in Placebo Patients | Risk Difference: Additional Drug Patients with Events per 1,000 Patients
Epilepsy | 1.0 | 3.4 | 3.5 | 2.4
Psychiatric | 5.7 | 8.5 | 1.5 | 2.9
Other | 1.0 | 1.8 | 1.9 | 0.9
Total | 2.4 | 4.3 | 1.8 | 1.9

The relative risk for suicidal thoughts or behavior was higher in clinical trials for epilepsy than in clinical trials for psychiatric or other conditions, but the absolute risk differences were similar for the epilepsy and psychiatric indications.

Anyone considering prescribing LAMICTAL XR or any other AED must balance the risk of suicidal thoughts or behavior with the risk of untreated illness. Epilepsy and many other illnesses for which AEDs are prescribed are themselves associated with morbidity and mortality and an increased risk of suicidal thoughts and behavior. Should suicidal thoughts and behavior emerge during treatment, the prescriber needs to consider whether the emergence of these symptoms in any given patient may be related to the illness being treated.

Patients, their caregivers, and families should be informed that AEDs increase the risk of suicidal thoughts and behavior and should be advised of the need to be alert for the emergence or worsening of the signs and symptoms of depression, any unusual changes in mood or behavior, the emergence of suicidal thoughts or suicidal behavior, or thoughts about self-harm. Behaviors of concern should be reported immediately to healthcare providers.

5.7 Aseptic Meningitis

Therapy with lamotrigine increases the risk of developing aseptic meningitis. Because of the potential for serious outcomes of untreated meningitis due to other causes, patients should also be evaluated for other causes of meningitis and treated as appropriate.

Postmarketing cases of aseptic meningitis have been reported in pediatric and adult patients taking lamotrigine for various indications. Symptoms upon presentation have included headache, fever, nausea, vomiting, and nuchal rigidity. Rash, photophobia, myalgia, chills, altered consciousness, and somnolence were also noted in some cases. Symptoms have been reported to occur within 1 day to one and a half months following the initiation of treatment. In most cases, symptoms were reported to resolve after discontinuation of lamotrigine. Re-exposure resulted in a rapid return of symptoms (from within 30 minutes to 1 day following re-initiation of treatment) that were frequently more severe. Some of the patients treated with lamotrigine who developed aseptic meningitis had underlying diagnoses of systemic lupus erythematosus or other autoimmune diseases.

Cerebrospinal fluid (CSF) analyzed at the time of clinical presentation in reported cases was characterized by a mild to moderate pleocytosis, normal glucose levels, and mild to moderate increase in protein. CSF white blood cell count differentials showed a predominance of neutrophils in a majority of the cases, although a predominance of lymphocytes was reported in approximately one third of the cases. Some patients also had new onset of signs and symptoms of involvement of other organs (predominantly hepatic and renal involvement), which may suggest that in these cases the aseptic meningitis observed was part of a hypersensitivity reaction [see Warnings and Precautions (5.3)].

5.8 Potential Medication Errors

Medication errors involving LAMICTAL XR have occurred. In particular, the names LAMICTAL or lamotrigine can be confused with the names of other commonly used medications. Medication errors may also occur between the different formulations of LAMICTAL. To reduce the potential of medication errors, write and say LAMICTAL XR clearly. Depictions of the LAMICTAL XR extended-release tablets can be found in the Medication Guide. Each LAMICTAL XR tablet has a distinct color and white center, and is printed with “LAMICTAL XR” and the tablet strength. These distinctive features serve to identify the different presentations of the drug and thus may help reduce the risk of medication errors. LAMICTAL XR is supplied in round, unit-of-use bottles with orange caps containing 30 tablets. The label on the bottle includes a depiction of the tablets that further communicates to patients and pharmacists that the medication is LAMICTAL XR and the specific tablet strength included in the bottle. The unit-of-use bottle with a distinctive orange cap and distinctive bottle label features serves to identify the different presentations of the drug and thus may help to reduce the risk of medication errors. To avoid the medication error of using the wrong drug or formulation, patients should be strongly advised to visually inspect their tablets to verify that they are LAMICTAL XR each time they fill their prescription.

5.9 Concomitant Use with Estrogen-Containing Products, Including Oral Contraceptives

Some estrogen-containing oral contraceptives have been shown to decrease serum concentrations of lamotrigine [see Clinical Pharmacology (12.3)]. Dosage adjustments will be necessary in most patients who start or stop estrogen-containing oral contraceptives while taking LAMICTAL XR [see Dosage and Administration (2.1)]. During the week of inactive hormone preparation (pill-free week) of oral contraceptive therapy, plasma lamotrigine levels are expected to rise, as much as doubling at the end of the week. Adverse reactions consistent with elevated levels of lamotrigine, such as dizziness, ataxia, and diplopia, could occur. Other oral contraceptive and other estrogen-containing therapies (such as HRT) have not been studied, though they may similarly affect lamotrigine pharmacokinetic parameters.

5.10 Withdrawal Seizures

As with other AEDs, LAMICTAL XR should not be abruptly discontinued. In patients with epilepsy there is a possibility of increasing seizure frequency. Unless safety concerns require a more rapid withdrawal, the dose of LAMICTAL XR should be tapered over a period of at least 2 weeks (approximately 50% reduction per week) [see Dosage and Administration (2.1)].

5.11 Status Epilepticus

Valid estimates of the incidence of treatment-emergent status epilepticus among patients treated with immediate-release lamotrigine are difficult to obtain because reporters participating in clinical trials did not all employ identical rules for identifying cases. At a minimum, 7 of 2,343 adult patients had episodes that could unequivocally be described as status epilepticus. In addition, a number of reports of variably defined episodes of seizure exacerbation (e.g., seizure clusters, seizure flurries) were made.

5.12 Addition of LAMICTAL XR to a Multidrug Regimen that Includes Valproate

Because valproate reduces the clearance of lamotrigine, the dosage of lamotrigine in the presence of valproate is less than half of that required in its absence [see Dosage and Administration (2.1, 2.2), Drug Interactions (7)].

5.13 Binding in the Eye and Other Melanin-Containing Tissues

Because lamotrigine binds to melanin, it could accumulate in melanin-rich tissues over time. This raises the possibility that lamotrigine may cause toxicity in these tissues after extended use. Although ophthalmological testing was performed in 1 controlled clinical trial, the testing was inadequate to exclude subtle effects or injury occurring after long-term exposure. Moreover, the capacity of available tests to detect potentially adverse consequences, if any, of lamotrigine’s binding to melanin is unknown.

Accordingly, although there are no specific recommendations for periodic ophthalmological monitoring, prescribers should be aware of the possibility of long-term ophthalmologic effects.

5.14 Laboratory Tests

False-Positive Drug Test Results

Lamotrigine has been reported to interfere with the assay used in some rapid urine drug screens, which can result in false-positive readings, particularly for phencyclidine (PCP). A more specific analytical method should be used to confirm a positive result.

Plasma Concentrations of Lamotrigine

The value of monitoring plasma concentrations of lamotrigine in patients treated with LAMICTAL XR has not been established. Because of the possible pharmacokinetic interactions between lamotrigine and other drugs, including AEDs (see Table 6), monitoring of the plasma levels of lamotrigine and concomitant drugs may be indicated, particularly during dosage adjustments. In general, clinical judgment should be exercised regarding monitoring of plasma levels of lamotrigine and other drugs and whether or not dosage adjustments are necessary.

Effect on Leukocytes

Treatment with LAMICTAL XR caused an increased incidence of subnormal (below the reference range) values in some hematology analytes (e.g., total white blood cells, monocytes). The treatment effect (LAMICTAL XR % - Placebo %) incidence of subnormal counts was 3% for total white blood cells and 4% for monocytes.

6 ADVERSE REACTIONS

The following serious adverse reactions are described in more detail in the Warnings and Precautions section of the labeling:

- Serious Skin Rashes [see Warnings and Precautions (5.1)]
- Hemophagocytic Lymphohistiocytosis [see Warnings and Precautions (5.2)]
- Multiorgan Hypersensitivity Reactions and Organ Failure [see Warnings and Precautions (5.3)]
- Cardiac Rhythm and Conduction Abnormalities [see Warnings and Precautions (5.4)]
- Blood Dyscrasias [see Warnings and Precautions (5.5)]
- Suicidal Behavior and Ideation [see Warnings and Precautions (5.6)]
- Aseptic Meningitis [see Warnings and Precautions (5.7)]
- Withdrawal Seizures [see Warnings and Precautions (5.10)]
- Status Epilepticus [see Warnings and Precautions (5.11)]

6.1 Clinical Trial Experience with LAMICTAL XR for Treatment of Primary Generalized Tonic-Clonic and Partial-Onset Seizures

Most Common Adverse Reactions in Clinical Trials

Adjunctive Therapy in Patients with Epilepsy: Because clinical trials are conducted under widely varying conditions, adverse reaction rates observed in the clinical trials of a drug cannot be directly compared with rates in the clinical trials of another drug and may not reflect the rates observed in practice.

In these 2 trials, adverse reactions led to withdrawal of 4 (2%) patients in the group receiving placebo and 10 (5%) patients in the group receiving LAMICTAL XR. Dizziness was the most common reason for withdrawal in the group receiving LAMICTAL XR (5 patients [3%]). The next most common adverse reactions leading to withdrawal in 2 patients each (1%) were rash, headache, nausea, and nystagmus.

Table 4 displays the incidence of adverse reactions in these two 19-week, double-blind, placebo-controlled trials of patients with PGTC and partial onset seizures.

Table 4. Adverse Reactions in Pooled, Placebo-Controlled, Adjunctive Trials in Patients with Epilepsya
Body System/ Adverse Reaction | Percent of Patients Receiving Adjunctive LAMICTAL XR (n = 190) | Percent of Patients Receiving Adjunctive Placebo (n = 195)
Ear and labyrinth disorders
Vertigo | 3 | <1
Eye disorders
Diplopia | 5 | <1
Vision blurred | 3 | 2
Gastrointestinal disorders
Nausea | 7 | 4
Vomiting | 6 | 3
Diarrhea | 5 | 3
Constipation | 2 | <1
Dry mouth | 2 | 1
General disorders and administration site conditions
Asthenia and fatigue | 6 | 4
Infections and infestations
Sinusitis | 2 | 1
Metabolic and nutritional disorders
Anorexia | 3 | 2
Musculoskeletal and connective tissue disorder
Myalgia | 2 | 0
Nervous system
Dizziness | 14 | 6
Tremor and intention tremor | 6 | 1
Somnolence | 5 | 3
Cerebellar coordination and balance disorder | 3 | 0
Nystagmus | 2 | <1
Psychiatric disorders
Depression | 3 | <1
Anxiety | 3 | 0
Respiratory, thoracic, and mediastinal disorders
Pharyngolaryngeal pain | 3 | 2
Vascular disorder
Hot flush | 2 | 0
a Adverse reactions that occurred in at least 2% of patients treated with LAMICTAL XR and at a greater incidence than placebo.

Note: In these trials the incidence of nonserious rash was 2% for LAMICTAL XR and 3% for placebo. In clinical trials evaluating immediate-release lamotrigine, the rate of serious rash was 0.3% in adults on adjunctive therapy for epilepsy [see Boxed Warning].

Adverse reactions were also analyzed to assess the incidence of the onset of an event in the titration period, and in the maintenance period, and if adverse reactions occurring in the titration phase persisted in the maintenance phase.

The incidence for many adverse reactions caused by treatment with LAMICTAL XR was increased relative to placebo (i.e., treatment difference between LAMICTAL XR and placebo ≥2%) in either the titration or maintenance phases of the trial. During the titration phase, an increased incidence (shown in descending order of percent treatment difference) was observed for diarrhea, nausea, vomiting, somnolence, vertigo, myalgia, hot flush, and anxiety. During the maintenance phase, an increased incidence was observed for dizziness, tremor, and diplopia. Some adverse reactions developing in the titration phase were notable for persisting (>7 days) into the maintenance phase. These persistent adverse reactions included somnolence and dizziness.

There were inadequate data to evaluate the effect of dose and/or concentration on the incidence of adverse reactions because, although patients were randomized to different target doses based upon concomitant AEDs, the plasma exposure was expected to be generally similar among all patients receiving different doses. However, in a randomized, parallel trial comparing placebo with 300 and 500 mg/day of immediate-release lamotrigine, the incidence of the most common adverse reactions (>5%) such as ataxia, blurred vision, diplopia, and dizziness were dose related. Less common adverse reactions (<5%) were not assessed for dose-response relationships.

Monotherapy in Patients with Epilepsy: Adverse reactions observed in this trial were generally similar to those observed and attributed to drug in adjunctive and monotherapy immediate-release lamotrigine and adjunctive LAMICTAL XR placebo-controlled trials. Only 2 adverse events, nasopharyngitis and upper respiratory tract infection, were observed at a rate of >3% and not reported at a similar rate in previous trials. Because this trial did not include a placebo control group, causality could not be established [see Clinical Studies (14.3)].

6.2 Other Adverse Reactions Observed during the Clinical Development of Immediate-Release Lamotrigine

All reported reactions are included except those already listed in the previous tables or elsewhere in the labeling, those too general to be informative, and those not reasonably associated with the use of the drug.

Adjunctive Therapy in Adults with Epilepsy

In addition to the adverse reactions reported above from the development of LAMICTAL XR, the following adverse reactions with an uncertain relationship to lamotrigine were reported during the clinical development of immediate-release lamotrigine for treatment of epilepsy in adults. These reactions occurred in ≥2% of patients receiving immediate-release lamotrigine and more frequently than in the placebo group.

Body as a Whole: Headache, flu syndrome, fever, neck pain.

Musculoskeletal: Arthralgia.

Nervous: Insomnia, convulsion, irritability, speech disorder, concentration disturbance.

Respiratory: Pharyngitis, cough increased.

Skin and Appendages: Rash, pruritus.

Urogenital (female patients only): Vaginitis, amenorrhea, dysmenorrhea.

Monotherapy in Adults with Epilepsy

In addition to the adverse reactions reported above from the development of LAMICTAL XR, the following adverse reactions with an uncertain relationship to lamotrigine were reported during the clinical development of immediate-release lamotrigine for treatment of epilepsy in adults. These reactions occurred in >2% of patients receiving immediate-release lamotrigine and more frequently than in the placebo group.

Body as a Whole: Chest pain.

Digestive: Rectal hemorrhage, peptic ulcer.

Metabolic and Nutritional: Weight decrease, peripheral edema.

Nervous: Hypesthesia, libido increase, decreased reflexes.

Respiratory: Epistaxis, dyspnea.

Skin and Appendages: Contact dermatitis, dry skin, sweating.

Special Senses: Vision abnormality.

Urogenital (female patients only): Dysmenorrhea.

Other Clinical Trial Experience

Immediate-release lamotrigine has been administered to 6,694 individuals for whom complete adverse reaction data was captured during all clinical trials, only some of which were placebo controlled.

Adverse reactions are further classified within body system categories and enumerated in order of decreasing frequency using the following definitions: frequent adverse reactions are defined as those occurring in at least 1/100 patients; infrequent adverse reactions are those occurring in 1/100 to 1/1,000 patients; rare adverse reactions are those occurring in fewer than 1/1,000 patients.

Cardiovascular System: Infrequent: Hypertension, palpitations, postural hypotension, syncope, tachycardia, vasodilation.

Dermatological: Infrequent: Acne, alopecia, hirsutism, maculopapular rash, urticaria.

Rare: Leukoderma, multiforme erythema, petechial rash, pustular rash.

Digestive System: Infrequent: Dysphagia, liver function tests abnormal, mouth ulceration.

Rare: Gastrointestinal hemorrhage, hemorrhagic colitis, hepatitis, melena, stomach ulcer.

Endocrine System: Rare: Goiter, hypothyroidism.

Hematologic and Lymphatic System: Infrequent: Ecchymosis, leukopenia.

Rare: Anemia, eosinophilia, fibrin decrease, fibrinogen decrease, iron deficiency anemia, leukocytosis, lymphocytosis, macrocytic anemia, petechia, thrombocytopenia.

Metabolic and Nutritional Disorders: Infrequent: Aspartate transaminase increased.

Rare: Alcohol intolerance, alkaline phosphatase increase, alanine transaminase increase, bilirubinemia, gamma glutamyl transpeptidase increase, hyperglycemia.

Musculoskeletal System: Rare: Muscle atrophy, pathological fracture, tendinous contracture.

Nervous System: Frequent: Confusion.

Infrequent: Akathisia, apathy, aphasia, depersonalization, dysarthria, dyskinesia, euphoria, hallucinations, hostility, hyperkinesia, hypertonia, libido decreased, memory decrease, mind racing, movement disorder, myoclonus, panic attack, paranoid reaction, personality disorder, psychosis, stupor.

Rare: Choreoathetosis, delirium, delusions, dysphoria, dystonia, extrapyramidal syndrome, hemiplegia, hyperalgesia, hyperesthesia, hypokinesia, hypotonia, manic depression reaction, neuralgia, paralysis, peripheral neuritis.

Respiratory System: Rare: Hiccup, hyperventilation.

Special Senses: Frequent: Amblyopia.

Infrequent: Abnormality of accommodation, conjunctivitis, dry eyes, ear pain, photophobia, taste perversion, tinnitus.

Rare: Deafness, lacrimation disorder, oscillopsia, parosmia, ptosis, strabismus, taste loss, uveitis, visual field defect.

Urogenital System: Infrequent: Abnormal ejaculation, hematuria, impotence, menorrhagia, polyuria, urinary incontinence.

Rare: Acute kidney failure, breast neoplasm, creatinine increase, female lactation, kidney failure, kidney pain, nocturia, urinary retention, urinary urgency.

6.3 Postmarketing Experience with Immediate-Release Lamotrigine

The following adverse reactions have been identified during postapproval use of immediate-release lamotrigine. Because these reactions are reported voluntarily from a population of uncertain size, it is not always possible to reliably estimate their frequency or establish a causal relationship to drug exposure.

Blood and Lymphatic

Agranulocytosis, hemolytic anemia, lymphadenopathy not associated with hypersensitivity disorder, pseudolymphoma.

Gastrointestinal

Esophagitis.

Hepatobiliary Tract and Pancreas

Pancreatitis.

Immunologic

Hypogammaglobulinemia, lupus-like reaction, vasculitis.

Lower Respiratory

Apnea.

Musculoskeletal

Rhabdomyolysis has been observed in patients experiencing hypersensitivity reactions.

Nervous System

Aggression, exacerbation of Parkinsonian symptoms in patients with pre-existing Parkinson’s disease, tics.

Non-site Specific

Progressive immunosuppression.

Renal and Urinary Disorders

Tubulointerstitial nephritis (has been reported alone and in association with uveitis).

Skin and subcutaneous tissue disorders

Photosensitivity reaction

7 DRUG INTERACTIONS

Significant drug interactions with lamotrigine are summarized in this section. Additional details of these drug interaction studies, which were conducted using immediate-release lamotrigine, are provided in the Clinical Pharmacology section [see Clinical Pharmacology (12.3)].

Uridine 5´-diphospho-glucuronyl transferases (UGT) have been identified as the enzymes responsible for metabolism of lamotrigine. Drugs that induce or inhibit glucuronidation may, therefore, affect the apparent clearance of lamotrigine. Strong or moderate inducers of the cytochrome P450 3A4 (CYP3A4) enzyme, which are also known to induce UGT, may also enhance the metabolism of lamotrigine.

Those drugs that have been demonstrated to have a clinically significant impact on lamotrigine metabolism are outlined in Table 13. Specific dosing guidance for these drugs is provided in the Dosage and Administration section, and, for women taking estrogen-containing products, including oral contraceptives, in the Warnings and Precautions section [see Dosage and Administration (2.1), Warnings and Precautions, (5.9)].

Table 5. Established and Other Potentially Significant Drug Interactions
Concomitant Drug | Effect on Concentration of Lamotrigine or Concomitant Drug | Clinical Comment
Estrogen-containing oral contraceptive preparations containing 30 mcg ethinylestradiol and 150 mcg levonorgestrel | ↓ lamotrigine | Decreased lamotrigine concentrations approximately 50%.
Estrogen-containing oral contraceptive preparations containing 30 mcg ethinylestradiol and 150 mcg levonorgestrel | ↓ levonorgestrel | Decrease in levonorgestrel component by 19%.
Carbamazepine and carbamazepine epoxide | ↓ lamotrigine | Addition of carbamazepine decreases lamotrigine concentration approximately 40%.
Carbamazepine and carbamazepine epoxide | ? carbamazepine epoxide | May increase carbamazepine epoxide levels.
Lopinavir/ritonavir | ↓ lamotrigine | Decreased lamotrigine concentration approximately 50%.
Atazanavir/ritonavir | ↓ lamotrigine | Decreased lamotrigine AUC approximately 32%.
Phenobarbital/primidone | ↓ lamotrigine | Decreased lamotrigine concentration approximately 40%.
Phenytoin | ↓ lamotrigine | Decreased lamotrigine concentration approximately 40%.
Rifampin | ↓ lamotrigine | Decreased lamotrigine AUC approximately 40%.
Valproate | ↑ lamotrigine | Increased lamotrigine concentrations slightly more than 2-fold.
Valproate | ? valproate | There are conflicting study results regarding effect of lamotrigine on valproate concentrations: 1) a mean 25% decrease in valproate concentrations in healthy volunteers, 2) no change in valproate concentrations in controlled clinical trials in patients with epilepsy.
↓ = Decreased (induces lamotrigine glucuronidation).
↑ = Increased (inhibits lamotrigine glucuronidation).
? = Conflicting data.

Effect of LAMICTAL XR on Organic Cationic Transporter 2 Substrates

Lamotrigine is an inhibitor of renal tubular secretion via organic cationic transporter 2 (OCT2) proteins [see Clinical Pharmacology (12.3)]. This may result in increased plasma levels of certain drugs that are substantially excreted via this route. Coadministration of LAMICTAL XR with OCT2 substrates with a narrow therapeutic index (e.g., dofetilide) is not recommended.

8 USE IN SPECIFIC POPULATIONS

8.1 Pregnancy

Pregnancy Exposure Registry

There is a pregnancy exposure registry that monitors pregnancy outcomes in women exposed to AEDs, including LAMICTAL XR, during pregnancy. Encourage women who are taking LAMICTAL XR during pregnancy to enroll in the North American Antiepileptic Drug (NAAED) Pregnancy Registry by calling 1-888-233-2334 or visiting http://www.aedpregnancyregistry.org/.

Risk Summary

Data from several prospective pregnancy exposure registries and epidemiological studies of pregnant women have not detected an increased frequency of major congenital malformations or a consistent pattern of malformations among women exposed to lamotrigine compared with the general population (see Data). In animal studies, administration of lamotrigine during pregnancy resulted in developmental toxicity (increased mortality, decreased body weight, increased structural variation, neurobehavioral abnormalities) at doses lower than those administered clinically.

Lamotrigine decreased fetal folate concentrations in rats, an effect known to be associated with adverse pregnancy outcomes in animals and humans (see Data).

In the U.S. general population, the estimated background risk of major birth defects and miscarriage in clinically recognized pregnancies is 2% to 4% and 15% to 20%, respectively.

Clinical Considerations

Disease-associated Maternal and/or Embryofetal Risk

Epilepsy, with or without exposure to antiepileptic drugs, has been associated with several adverse outcomes during pregnancy, including preeclampsia, preterm labor, antepartum and postpartum hemorrhage, placental abruption, poor fetal growth, prematurity, fetal death, and maternal mortality. The risk of maternal or fetal injury may be greatest for patients with untreated or poorly controlled convulsive seizures. Women with epilepsy who become pregnant should not abruptly discontinue antiepileptic drugs, including LAMICTAL XR, due to the risk of status epilepticus or severe seizures, which may be life-threatening [see Warnings and Precautions (5.10)].

Dose Adjustments During Pregnancy and the Postpartum Period

As with other AEDs, physiological changes during pregnancy may affect lamotrigine concentrations and/or therapeutic effect. There have been reports of decreased lamotrigine concentrations during pregnancy and restoration of pre-pregnancy concentrations after delivery. Dose adjustments may be necessary to maintain clinical response.

Data

Human Data: Data from several international pregnancy registries have not shown an increased risk for malformations overall. The International Lamotrigine Pregnancy Registry reported major congenital malformations in 2.2% (95% CI: 1.6%, 3.1%) of 1,558 infants exposed to lamotrigine monotherapy in the first trimester of pregnancy. The NAAED Pregnancy Registry reported major congenital malformations among 2.0% of 1,562 infants exposed to lamotrigine monotherapy in the first trimester. EURAP, a large international pregnancy registry focused outside of North America, reported major birth defects in 2.9% (95% CI: 2.3%, 3.7%) of 2,514 exposures to lamotrigine monotherapy in the first trimester. The frequency of major congenital malformations was similar to estimates from the general population.

The NAAED Pregnancy Registry observed an increased risk of isolated oral clefts: among 2,200 infants exposed to lamotrigine early in pregnancy, the risk of oral clefts was 3.2 per 1,000 (95% CI: 1.4, 6.3), a 3-fold increased risk versus unexposed healthy controls. This finding has not been observed in other large international pregnancy registries. Furthermore, a case-control study based on 21 congenital anomaly registries covering over 10 million births in Europe reported an adjusted odds ratio for isolated oral clefts with lamotrigine exposure of 1.45 (95% CI: 0.8, 2.63).

Several meta-analyses have not reported an increased risk of major congenital malformations following lamotrigine exposure in pregnancy compared with healthy and disease-matched controls. No patterns of specific malformation types were observed.

The same meta-analyses evaluated the risk of additional maternal and infant outcomes including fetal death, stillbirth, preterm birth, small for gestational age, and neurodevelopmental delay. Although there are no data suggesting an increased risk of these outcomes with lamotrigine monotherapy exposure, differences in outcome definition, ascertainment methods, and comparator groups limit the conclusions that can be drawn.

Animal Data: When lamotrigine was administered to pregnant mice, rats, or rabbits during the period of organogenesis (oral doses of up to 125, 25, and 30 mg/kg, respectively), reduced fetal body weight and increased incidences of fetal skeletal variations were seen in mice and rats at doses that were also maternally toxic. The no-effect doses for embryofetal developmental toxicity in mice, rats, and rabbits (75, 6.25, and 30 mg/kg, respectively) are similar to (mice and rabbits) or less than (rats) the human dose of 400 mg/day on a body surface area (mg/m^2) basis.

In a study in which pregnant rats were administered lamotrigine (oral doses of 0, 5, or 25 mg/kg) during the period of organogenesis and offspring were evaluated postnatally, neurobehavioral abnormalities were observed in exposed offspring at both doses. The lowest effect dose for developmental neurotoxicity in rats is less than the human dose of 400 mg/day on a mg/m^2 basis. Maternal toxicity was observed at the higher dose tested.

When pregnant rats were administered lamotrigine (oral doses of 0, 5, 10, or 20 mg/kg) during the latter part of gestation and throughout lactation, increased offspring mortality (including stillbirths) was seen at all doses. The lowest effect dose for pre- and post-natal developmental toxicity in rats is less than the human dose of 400 mg/day on a mg/m^2 basis. Maternal toxicity was observed at the 2 highest doses tested.

When administered to pregnant rats, lamotrigine decreased fetal folate concentrations at doses greater than or equal to 5 mg/kg/day, which is less than the human dose of 400 mg/day on a mg/m^2 basis.

8.2 Lactation

Risk Summary

Lamotrigine is present in milk from lactating women taking LAMICTAL XR (see Data). Neonates and young infants are at risk for high serum levels because maternal serum and milk levels can rise to high levels postpartum if lamotrigine dosage has been increased during pregnancy but is not reduced after delivery to the pre-pregnancy dosage. Glucuronidation is required for drug clearance. Glucuronidation capacity is immature in the infant and this may also contribute to the level of lamotrigine exposure. Events including rash, apnea, drowsiness, poor sucking, and poor weight gain (requiring hospitalization in some cases) have been reported in infants who have been human milk-fed by mothers using lamotrigine; whether or not these events were caused by lamotrigine is unknown. No data are available on the effects of the drug on milk production.

The developmental and health benefits of breastfeeding should be considered along with the mother’s clinical need for LAMICTAL XR and any potential adverse effects on the breastfed infant from LAMICTAL XR or from the underlying maternal condition.

Clinical Considerations

Human milk-fed infants should be closely monitored for adverse events resulting from lamotrigine. Measurement of infant serum levels should be performed to rule out toxicity if concerns arise. Human milk-feeding should be discontinued in infants with lamotrigine toxicity.

Data

Data from multiple small studies indicate that lamotrigine plasma levels in nursing infants have been reported to be as high as 50% of maternal plasma concentrations.

8.4 Pediatric Use

LAMICTAL XR is indicated as adjunctive therapy for PGTC and partial-onset seizures with or without secondary generalization in patients aged 13 years and older. Safety and effectiveness of LAMICTAL XR for any use in patients younger than 13 years have not been established.

Immediate-release lamotrigine is indicated as adjunctive therapy in patients aged 2 years and older for partial-onset seizures, the generalized seizures of Lennox-Gastaut syndrome, and PGTC seizures.

Safety and efficacy of immediate-release lamotrigine used as adjunctive treatment for partial-onset seizures were not demonstrated in a small, randomized, double-blind, placebo-controlled withdrawal trial in very young pediatric patients (aged 1 to 24 months). Immediate-release lamotrigine was associated with an increased risk for infectious adverse reactions (lamotrigine 37%, placebo 5%), and respiratory adverse reactions (lamotrigine 26%, placebo 5%). Infectious adverse reactions included bronchiolitis, bronchitis, ear infection, eye infection, otitis externa, pharyngitis, urinary tract infection, and viral infection. Respiratory adverse reactions included nasal congestion, cough, and apnea.

Juvenile Animal Data

In a juvenile animal study in which lamotrigine (oral doses of 0, 5, 15, or 30 mg/kg) was administered to young rats from postnatal day 7 to 62, decreased viability and growth were seen at the highest dose tested and long-term neurobehavioral abnormalities (decreased locomotor activity, increased reactivity, and learning deficits in animals tested as adults) were observed at the 2 highest doses. The no-effect dose for adverse developmental effects in juvenile animals is less than the human dose of 400 mg/day on a mg/m^2 basis.

8.5 Geriatric Use

Clinical trials of LAMICTAL XR for epilepsy did not include sufficient numbers of patients aged 65 years and older to determine whether they respond differently from younger patients or exhibit a different safety profile than that of younger patients. In general, dose selection for an elderly patient should be cautious, usually starting at the low end of the dosing range, reflecting the greater frequency of decreased hepatic, renal, or cardiac function and of concomitant disease or other drug therapy.

8.6 Hepatic Impairment

Experience in patients with hepatic impairment is limited. Based on a clinical pharmacology study with immediate-release lamotrigine in 24 subjects with mild, moderate, and severe liver impairment, the following general recommendations can be made [see Clinical Pharmacology (12.3)]. No dosage adjustment is needed in patients with mild liver impairment. Initial, escalation, and maintenance doses should generally be reduced by approximately 25% in patients with moderate and severe liver impairment without ascites and 50% in patients with severe liver impairment with ascites. Escalation and maintenance doses may be adjusted according to clinical response [see Dosage and Administration (2.1)].

8.7 Renal Impairment

Lamotrigine is metabolized mainly by glucuronic acid conjugation, with the majority of the metabolites being recovered in the urine. In a small study comparing a single dose of immediate-release lamotrigine in subjects with varying degrees of renal impairment with healthy volunteers, the plasma half-life of lamotrigine was approximately twice as long in the subjects with chronic renal failure [see Clinical Pharmacology (12.3)].

Initial doses of LAMICTAL XR should be based on patients’ AED regimens; reduced maintenance doses may be effective for patients with significant renal impairment. Few patients with severe renal impairment have been evaluated during chronic treatment with lamotrigine. Because there is inadequate experience in this population, LAMICTAL XR should be used with caution in these patients [see Dosage and Administration (2.1)].

10 OVERDOSAGE

10.1 Human Overdose Experience

Overdoses involving quantities up to 15 g have been reported for immediate-release lamotrigine, some of which have been fatal. Overdose has resulted in ataxia, nystagmus, seizures (including tonic-clonic seizures), decreased level of consciousness, coma, and intraventricular conduction delay.

10.2 Management of Overdose

There are no specific antidotes for lamotrigine. Following a suspected overdose, hospitalization of the patient is advised. General supportive care is indicated, including frequent monitoring of vital signs and close observation of the patient. If indicated, emesis should be induced; usual precautions should be taken to protect the airway. It is uncertain whether hemodialysis is an effective means of removing lamotrigine from the blood. In 6 renal failure patients, about 20% of the amount of lamotrigine in the body was removed by hemodialysis during a 4-hour session. A Poison Control Center should be contacted for information on the management of overdosage of LAMICTAL XR.

11 DESCRIPTION

LAMICTAL XR (lamotrigine), an AED of the phenyltriazine class, is chemically unrelated to existing AEDs. Lamotrigine’s chemical name is 3,5-diamino-6-(2,3-dichlorophenyl)-as-triazine, its molecular formula is C9H7N5Cl2, and its molecular weight is 256.09. Lamotrigine is a white to pale cream-colored powder and has a pKa of 5.7. Lamotrigine is very slightly soluble in water (0.17 mg/mL at 25°C) and slightly soluble in 0.1 M HCl (4.1 mg/mL at 25°C). The structural formula is:

LAMICTAL XR extended-release tablets are supplied for oral administration as 25-mg (yellow with white center), 50-mg (green with white center), 100-mg (orange with white center), 200-mg (blue with white center), 250-mg (purple with white center), and 300-mg (gray with white center) tablets. Each tablet contains the labeled amount of lamotrigine and the following inactive ingredients: glycerol monostearate, hypromellose, lactose monohydrate; magnesium stearate; methacrylic acid copolymer dispersion, polyethylene glycol 400, polysorbate 80, silicon dioxide (25- and 50-mg tablets only), titanium dioxide, triethyl citrate, carmine (250-mg tablet only), iron oxide black (50-, 250-, and 300-mg tablets only), iron oxide yellow (25-, 50-, and 100-mg tablets only), iron oxide red (100-mg tablet only), FD&C Blue No. 2 Aluminum Lake (200- and 250-mg tablets only). Tablets are printed with edible black ink.

LAMICTAL XR extended-release tablets contain a modified-release eroding formulation as the core. The tablets are coated with a clear enteric coat and have an aperture drilled through the coats on both faces of the tablet (DiffCORE) to enable a controlled release of drug in the acidic environment of the stomach. The combination of this and the modified-release core are designed to control the dissolution rate of lamotrigine over a period of approximately 12 to 15 hours, leading to a gradual increase in serum lamotrigine levels.

12 CLINICAL PHARMACOLOGY

12.1 Mechanism of Action

The precise mechanism(s) by which lamotrigine exerts its anticonvulsant action are unknown. In animal models designed to detect anticonvulsant activity, lamotrigine was effective in preventing seizure spread in the maximum electroshock (MES) and pentylenetetrazol (scMet) tests, and prevented seizures in the visually and electrically evoked after-discharge (EEAD) tests for antiepileptic activity. Lamotrigine also displayed inhibitory properties in the kindling model in rats both during kindling development and in the fully kindled state. The relevance of these models to human epilepsy, however, is not known.

One proposed mechanism of action of lamotrigine, the relevance of which remains to be established in humans, involves an effect on sodium channels. In vitro pharmacological studies suggest that lamotrigine inhibits voltage-sensitive sodium channels, thereby stabilizing neuronal membranes and consequently modulating presynaptic transmitter release of excitatory amino acids (e.g., glutamate and aspartate).

Effect of Lamotrigine on N-Methyl d-Aspartate-Receptor–Mediated Activity

Lamotrigine did not inhibit N-methyl d-aspartate (NMDA)-induced depolarizations in rat cortical slices or NMDA-induced cyclic GMP formation in immature rat cerebellum, nor did lamotrigine displace compounds that are either competitive or noncompetitive ligands at this glutamate receptor complex (CNQX, CGS, TCHP). The IC50 for lamotrigine effects on NMDA-induced currents (in the presence of 3 µM of glycine) in cultured hippocampal neurons exceeded 100 µM.

12.2 Pharmacodynamics

Folate Metabolism

In vitro, lamotrigine inhibited dihydrofolate reductase, the enzyme that catalyzes the reduction of dihydrofolate to tetrahydrofolate. Inhibition of this enzyme may interfere with the biosynthesis of nucleic acids and proteins. When oral daily doses of lamotrigine were given to pregnant rats during organogenesis, fetal, placental, and maternal folate concentrations were reduced. Significantly reduced concentrations of folate are associated with teratogenesis [see Use in Specific Populations (8.1)]. Folate concentrations were also reduced in male rats given repeated oral doses of lamotrigine. Reduced concentrations were partially returned to normal when supplemented with folinic acid.

Cardiac Electrophysiology

Effect of Lamotrigine: In vitro studies show that lamotrigine exhibits Class IB antiarrhythmic activity at therapeutically relevant concentrations. It inhibits human cardiac sodium channels with rapid onset and offset kinetics and strong voltage dependence, consistent with other Class IB antiarrhythmic agents. At therapeutic doses, LAMICTAL XR did not slow ventricular conduction (widen QRS) in healthy individuals in a thorough QT study; however, in patients with clinically important structural or functional heart disease or (i.e., patients with heart failure, valvular heart disease, congenital heart disease, conduction system disease, ventricular arrhythmias, cardiac channelopathies [e.g., Brugada syndrome], clinically important ischemic heart disease, or multiple risk factors for coronary artery disease), LAMICTAL XR could slow ventricular conduction (widen QRS) and induce proarrhythmia, which can lead to sudden death. Elevated heart rates could also increase the risk of ventricular conduction slowing with LAMICTAL XR.

Effect of Lamotrigine Metabolite: In dogs, lamotrigine is extensively metabolized to a 2-N-methyl metabolite. This metabolite causes dose-dependent prolongation of the PR interval, widening of the QRS complex, and, at higher doses, complete AV conduction block. The in vitro electrophysiological effects of this metabolite have not been studied. Similar cardiovascular effects from this metabolite are not anticipated in humans because only trace amounts of the 2-N-methyl metabolite (<0.6% of lamotrigine dose) have been found in human urine [see Clinical Pharmacology (12.3)]. However, it is conceivable that plasma concentrations of this metabolite could be increased in patients with a reduced capacity to glucuronidate lamotrigine (e.g., in patients with liver disease, patients taking concomitant medications that inhibit glucuronidation).

12.3 Pharmacokinetics

In comparison with immediate-release lamotrigine, the plasma lamotrigine levels following administration of LAMICTAL XR are not associated with any significant changes in trough plasma concentrations, and are characterized by lower peaks, longer time to peaks, and lower peak-to-trough fluctuation, as described in detail below.

Absorption

Lamotrigine is absorbed after oral administration with negligible first-pass metabolism. The bioavailability of lamotrigine is not affected by food.

In an open-label, crossover study of 44 subjects with epilepsy receiving concomitant AEDs, the steady-state pharmacokinetics of lamotrigine were compared following administration of equivalent total doses of LAMICTAL XR given once daily with those of lamotrigine immediate-release given twice daily. In this study, the median time to peak concentration (Tmax) following administration of LAMICTAL XR was 4 to 6 hours in subjects taking carbamazepine, phenytoin, phenobarbital, or primidone; 9 to 11 hours in subjects taking valproate; and 6 to 10 hours in subjects taking AEDs other than carbamazepine, phenytoin, phenobarbital, primidone, or valproate. In comparison, the median Tmax following administration of immediate-release lamotrigine was between 1 and 1.5 hours.

The steady-state trough concentrations for extended-release lamotrigine were similar to or higher than those of immediate-release lamotrigine depending on concomitant AED (see Table 6). A mean reduction in the lamotrigine Cmax by 11% to 29% was observed for LAMICTAL XR compared with immediate-release lamotrigine, resulting in a decrease in the peak-to-trough fluctuation in serum lamotrigine concentrations. However, in some subjects receiving enzyme-inducing AEDs, a reduction in Cmax of 44% to 77% was observed. The degree of fluctuation was reduced by 17% in subjects taking enzyme-inducing AEDs; 34% in subjects taking valproate; and 37% in subjects taking AEDs other than carbamazepine, phenytoin, phenobarbital, primidone, or valproate. LAMICTAL XR and immediate-release lamotrigine regimens were similar with respect to area under the curve (AUC, a measure of the extent of bioavailability) for subjects receiving AEDs other than those known to induce the metabolism of lamotrigine. The relative bioavailability of extended-release lamotrigine was approximately 21% lower than immediate-release lamotrigine in subjects receiving enzyme-inducing AEDs. However, a reduction in exposure of up to 70% was observed in some subjects in this group when they switched to LAMICTAL XR. Therefore, doses may need to be adjusted in some patients based on therapeutic response.

Table 6. Steady-State Bioavailability of LAMICTAL XR Relative to Immediate-Release Lamotrigine at Equivalent Daily Doses (Ratio of Extended-Release to Immediate-Release 90% CI)
Concomitant Antiepileptic Drug | AUC(0-24ss) | Cmax | Cmin
Enzyme-inducing antiepileptic drugsa | 0.79 (0.69, 0.90) | 0.71 (0.61, 0.82) | 0.99 (0.89, 1.09)
Valproate | 0.94 (0.81, 1.08) | 0.88 (0.75, 1.03) | 0.99 (0.88, 1.10)
Antiepileptic drugs other than enzyme-inducing antiepileptic drugsa or valproate | 1.00 (0.88, 1.14) | 0.89 (0.78, 1.03) | 1.14 (1.03, 1.25)
a Enzyme-inducing AEDs include carbamazepine, phenytoin, phenobarbital, and primidone.

Dose Proportionality

In healthy volunteers not receiving any other medications and given LAMICTAL XR once daily, the systemic exposure to lamotrigine increased in direct proportion to the dose administered over the range of 50 to 200 mg. At doses between 25 and 50 mg, the increase was less than dose proportional, with a 2-fold increase in dose resulting in an approximately 1.6-fold increase in systemic exposure.

Distribution

Estimates of the mean apparent volume of distribution (Vd/F) of lamotrigine following oral administration ranged from 0.9 to 1.3 L/kg. Vd/F is independent of dose and is similar following single and multiple doses in both patients with epilepsy and in healthy volunteers.

Protein Binding

Data from in vitro studies indicate that lamotrigine is approximately 55% bound to human plasma proteins at plasma lamotrigine concentrations from 1 to 10 mcg/mL (10 mcg/mL is 4 to 6 times the trough plasma concentration observed in the controlled efficacy trials). Because lamotrigine is not highly bound to plasma proteins, clinically significant interactions with other drugs through competition for protein binding sites are unlikely. The binding of lamotrigine to plasma proteins did not change in the presence of therapeutic concentrations of phenytoin, phenobarbital, or valproate. Lamotrigine did not displace other AEDs (carbamazepine, phenytoin, phenobarbital) from protein-binding sites.

Metabolism

Lamotrigine is metabolized predominantly by glucuronic acid conjugation; the major metabolite is an inactive 2-N-glucuronide conjugate. After oral administration of 240 mg of ^14C-lamotrigine (15 μCi) to 6 healthy volunteers, 94% was recovered in the urine and 2% was recovered in the feces. The radioactivity in the urine consisted of unchanged lamotrigine (10%), the 2-N-glucuronide (76%), a 5-N-glucuronide (10%), a 2-N-methyl metabolite (0.14%), and other unidentified minor metabolites (4%).

Enzyme Induction

The effects of lamotrigine on the induction of specific families of mixed-function oxidase isozymes have not been systematically evaluated.

Following multiple administrations (150 mg twice daily) to normal volunteers taking no other medications, lamotrigine induced its own metabolism, resulting in a 25% decrease in t½ and a 37% increase in CL/F at steady state compared with values obtained in the same volunteers following a single dose. Evidence gathered from other sources suggests that self-induction by lamotrigine may not occur when lamotrigine is given as adjunctive therapy in patients receiving enzyme-inducing drugs such as carbamazepine, phenytoin, phenobarbital, primidone, or other drugs such as rifampin and the protease inhibitors lopinavir/ritonavir and atazanavir/ritonavir that induce lamotrigine glucuronidation [see Drug Interactions (7)].

Elimination

The elimination half-life and apparent clearance of lamotrigine following oral administration of immediate-release lamotrigine to adult subjects with epilepsy and healthy volunteers is summarized in Table 7. Half-life and apparent oral clearance vary depending on concomitant AEDs.

Since the half-life of lamotrigine following administration of single doses of immediate-release lamotrigine is comparable with that observed following administration of LAMICTAL XR, similar changes in the half-life of lamotrigine would be expected for LAMICTAL XR.

Table 7. Mean Pharmacokinetic Parametersa of Immediate-Release Lamotrigine in Healthy Volunteers and Adult Subjects with Epilepsy
Adult Study Population | Number of Subjects | t½: Elimination Half‑life (h) | CL/F: Apparent Plasma Clearance (mL/min/kg)
Healthy volunteers taking no other medications:
Single-dose lamotrigine | 179 | 32.8; (14.0-103.0) | 0.44; (0.12-1.10)
Multiple-dose lamotrigine | 36 | 25.4; (11.6-61.6) | 0.58; (0.24-1.15)
Healthy volunteers taking valproate:
Single-dose lamotrigine | 6 | 48.3; (31.5-88.6) | 0.30; (0.14-0.42)
Multiple-dose lamotrigine | 18 | 70.3; (41.9-113.5) | 0.18; (0.12-0.33)
Subjects with epilepsy taking valproate only:
Single-dose lamotrigine | 4 | 58.8; (30.5-88.8) | 0.28; (0.16-0.40)
Subjects with epilepsy taking carbamazepine, phenytoin, phenobarbital, or primidoneb plus valproate:
Single-dose lamotrigine | 25 | 27.2; (11.2-51.6) | 0.53; (0.27-1.04)
Subjects with epilepsy taking carbamazepine, phenytoin, phenobarbital, or primidone:b
Single-dose lamotrigine | 24 | 14.4; (6.4-30.4) | 1.10; (0.51-2.22)
Multiple-dose lamotrigine | 17 | 12.6; (7.5-23.1) | 1.21; (0.66-1.82)
a The majority of parameter means determined in each study had coefficients of variation between 20% and 40% for half-life and CL/F and between 30% and 70% for Tmax. The overall mean values were calculated from individual study means that were weighted based on the number of volunteers/subjects in each study. The numbers in parentheses below each parameter mean represent the range of individual volunteer/subject values across studies.
b Carbamazepine, phenytoin, phenobarbital, and primidone have been shown to increase the apparent clearance of lamotrigine. Estrogen-containing oral contraceptives and other drugs, such as rifampin and protease inhibitors lopinavir/ritonavir and atazanavir/ritonavir, that induce lamotrigine glucuronidation have also been shown to increase the apparent clearance of lamotrigine [see Drug Interactions (7)].

Drug Interactions

The apparent clearance of lamotrigine is affected by the coadministration of certain medications [see Warnings and Precautions (5.9, 5.12), Drug Interactions (7)].

The net effects of drug interactions with lamotrigine, based on drug interaction studies using immediate-release lamotrigine, are summarized in Tables 5 and 8, followed by details of the drug interaction studies below.

Table 8. Summary of Drug Interactions with Lamotrigine
Drug | Drug Plasma Concentration with Adjunctive Lamotriginea | Lamotrigine Plasma Concentration with Adjunctive Drugsb
Oral contraceptives (e.g., ethinylestradiol/levonorgestrel)c | ↔d | ↓
Aripiprazole | Not assessed | ↔e
Atazanavir/ritonavir | ↔f | ↓
Bupropion | Not assessed | ↔
Carbamazepine | ↔ | ↓
Carbamazepine epoxideg | ?
Felbamate | Not assessed | ↔
Gabapentin | Not assessed | ↔
Lacosamide | Not assessed | ↔
Levetiracetam | ↔ | ↔
Lithium | ↔ | Not assessed
Lopinavir/ritonavir | ↔e | ↓
Olanzapine | ↔ | ↔e
Oxcarbazepine | ↔ | ↔
10-Monohydroxy oxcarbazepine metaboliteh | ↔
Perampanel | Not assessed | ↔e
Phenobarbital/primidone | ↔ | ↓
Phenytoin | ↔ | ↓
Pregabalin | ↔ | ↔
Rifampin | Not assessed | ↓
Risperidone | ↔ | Not assessed
9-Hydroxyrisperidonei | ↔
Topiramate | ↔j | ↔
Valproate | ↓ | ↑
Valproate + phenytoin and/or carbamazepine | Not assessed | ↔
Zonisamide | Not assessed | ↔
a From adjunctive clinical trials and volunteer trials.
b Net effects were estimated by comparing the mean clearance values obtained in adjunctive clinical trials and volunteer trials.
c The effect of other hormonal contraceptive preparations or HRT on the pharmacokinetics of lamotrigine has not been systematically evaluated in clinical trials, although the effect may be similar to that seen with the ethinylestradiol/levonorgestrel combinations.
d Modest decrease in levonorgestrel.
e Slight decrease, not expected to be clinically meaningful.
f Compared with historical controls.
g Not administered, but an active metabolite of carbamazepine.
h Not administered, but an active metabolite of oxcarbazepine.
i Not administered, but an active metabolite of risperidone.
j Slight increase, not expected to be clinically meaningful.
↔ = No significant effect.
? = Conflicting data.

Estrogen-Containing Oral Contraceptives

In 16 female volunteers, an oral contraceptive preparation containing 30 mcg ethinylestradiol and 150 mcg levonorgestrel increased the apparent clearance of lamotrigine (300 mg/day) by approximately 2-fold with mean decreases in AUC of 52% and in Cmax of 39%. In this study, trough serum lamotrigine concentrations gradually increased and were approximately 2-fold higher on average at the end of the week of the inactive hormone preparation compared with trough lamotrigine concentrations at the end of the active hormone cycle.

Gradual transient increases in lamotrigine plasma levels (approximate 2-fold increase) occurred during the week of inactive hormone preparation (pill-free week) for women not also taking a drug that increased the clearance of lamotrigine (carbamazepine, phenytoin, phenobarbital, primidone, or other drugs such as rifampin and the protease inhibitors lopinavir/ritonavir and atazanavir/ritonavir that induce lamotrigine glucuronidation) [see Drug Interactions (7)]. The increase in lamotrigine plasma levels will be greater if the dose of LAMICTAL XR is increased in the few days before or during the pill-free week. Increases in lamotrigine plasma levels could result in dose-dependent adverse reactions.

In the same study, coadministration of lamotrigine (300 mg/day) in 16 female volunteers did not affect the pharmacokinetics of the ethinylestradiol component of the oral contraceptive preparation. There were mean decreases in the AUC and Cmax of the levonorgestrel component of 19% and 12%, respectively. Measurement of serum progesterone indicated that there was no hormonal evidence of ovulation in any of the 16 volunteers, although measurement of serum FSH, LH, and estradiol indicated that there was some loss of suppression of the hypothalamic-pituitary-ovarian axis.

The effects of doses of lamotrigine other than 300 mg/day have not been systematically evaluated in controlled clinical trials. Studies with other female hormonal preparations (including progesterone/progesterone-containing HRT) have not been conducted.

The clinical significance of the observed hormonal changes on ovulatory activity is unknown. However, the possibility of decreased contraceptive efficacy in some patients cannot be excluded. Therefore, patients should be instructed to promptly report changes in their menstrual pattern (e.g., break-through bleeding).

Dosage adjustments may be necessary for women receiving estrogen-containing products, including oral contraceptive preparations [see Dosage and Administration (2.1)].

Other Hormonal Contraceptives or Hormone Replacement Therapy

The effect of other hormonal contraceptive preparations or HRT on the pharmacokinetics of lamotrigine has not been systematically evaluated. It has been reported that ethinylestradiol, not progestogens, increased the clearance of lamotrigine up to 2-fold, and the progestin-only pills had no effect on lamotrigine plasma levels. Therefore, adjustments to the dosage of LAMICTAL XR in the presence of progestogens alone will likely not be needed.

Aripiprazole

In 18 patients with bipolar disorder on a stable regimen of 100 to 400 mg/day of lamotrigine, the lamotrigine AUC and Cmax were reduced by approximately 10% in patients who received aripiprazole 10 to 30 mg/day for 7 days, followed by 30 mg/day for an additional 7 days. This reduction in lamotrigine exposure is not considered clinically meaningful.

Atazanavir/Ritonavir

In a study in healthy volunteers, daily doses of atazanavir/ritonavir (300 mg/100 mg) reduced the plasma AUC and Cmax of lamotrigine (single 100-mg dose) by an average of 32% and 6%, respectively, and shortened the elimination half-lives by 27%. In the presence of atazanavir/ritonavir (300 mg/100 mg), the metabolite-to-lamotrigine ratio was increased from 0.45 to 0.71 consistent with induction of glucuronidation. The pharmacokinetics of atazanavir/ritonavir were similar in the presence of concomitant lamotrigine to the historical data of the pharmacokinetics in the absence of lamotrigine.

Bupropion

The pharmacokinetics of a 100-mg single dose of lamotrigine in healthy volunteers (n = 12) were not changed by coadministration of bupropion sustained-release formulation (150 mg twice daily) starting 11 days before lamotrigine.

Carbamazepine

Lamotrigine has no appreciable effect on steady-state carbamazepine plasma concentration. Limited clinical data suggest there is a higher incidence of dizziness, diplopia, ataxia, and blurred vision in patients receiving carbamazepine with lamotrigine than in patients receiving other AEDs with lamotrigine [see Adverse Reactions (6.1)]. The mechanism of this interaction is unclear. The effect of lamotrigine on plasma concentrations of carbamazepine-epoxide is unclear. In a small subset of patients (n = 7) studied in a placebo-controlled trial, lamotrigine had no effect on carbamazepine-epoxide plasma concentrations, but in a small, uncontrolled study (n = 9), carbamazepine-epoxide levels increased.

The addition of carbamazepine decreases lamotrigine steady-state concentrations by approximately 40%.

Esomeprazole

In a study of 30 subjects, coadministration of LAMICTAL XR with esomeprazole resulted in no significant change in lamotrigine levels and a small decrease in Tmax. The levels of gastric pH were not altered compared with pre-lamotrigine dosing.

Felbamate

In a trial in 21 healthy volunteers, coadministration of felbamate (1,200 mg twice daily) with lamotrigine (100 mg twice daily for 10 days) appeared to have no clinically relevant effects on the pharmacokinetics of lamotrigine.

Folate Inhibitors

Lamotrigine is a weak inhibitor of dihydrofolate reductase. Prescribers should be aware of this action when prescribing other medications that inhibit folate metabolism.

Gabapentin

Based on a retrospective analysis of plasma levels in 34 subjects who received lamotrigine both with and without gabapentin, gabapentin does not appear to change the apparent clearance of lamotrigine.

Lacosamide

Plasma concentrations of lamotrigine were not affected by concomitant lacosamide (200, 400, or 600 mg/day) in placebo-controlled clinical trials in patients with partial-onset seizures.

Levetiracetam

Potential drug interactions between levetiracetam and lamotrigine were assessed by evaluating serum concentrations of both agents during placebo-controlled clinical trials. These data indicate that lamotrigine does not influence the pharmacokinetics of levetiracetam and that levetiracetam does not influence the pharmacokinetics of lamotrigine.

Lithium

The pharmacokinetics of lithium were not altered in healthy subjects (n = 20) by coadministration of lamotrigine (100 mg/day) for 6 days.

Lopinavir/Ritonavir

The addition of lopinavir (400 mg twice daily)/ritonavir (100 mg twice daily) decreased the AUC, Cmax, and elimination half-life of lamotrigine by approximately 50% to 55.4% in 18 healthy subjects. The pharmacokinetics of lopinavir/ritonavir were similar with concomitant lamotrigine, compared with that in historical controls.

Olanzapine

The AUC and Cmax of olanzapine were similar following the addition of olanzapine (15 mg once daily) to lamotrigine (200 mg once daily) in healthy male volunteers (n = 16) compared with the AUC and Cmax in healthy male volunteers receiving olanzapine alone (n = 16).

In the same trial, the AUC and Cmax of lamotrigine were reduced on average by 24% and 20%, respectively, following the addition of olanzapine to lamotrigine in healthy male volunteers compared with those receiving lamotrigine alone. This reduction in lamotrigine plasma concentrations is not expected to be clinically meaningful.

Oxcarbazepine

The AUC and Cmax of oxcarbazepine and its active 10-monohydroxy oxcarbazepine metabolite were not significantly different following the addition of oxcarbazepine (600 mg twice daily) to lamotrigine (200 mg once daily) in healthy male volunteers (n = 13) compared with healthy male volunteers receiving oxcarbazepine alone (n = 13).

In the same trial, the AUC and Cmax of lamotrigine were similar following the addition of oxcarbazepine (600 mg twice daily) to lamotrigine in healthy male volunteers compared with those receiving lamotrigine alone. Limited clinical data suggest a higher incidence of headache, dizziness, nausea, and somnolence with coadministration of lamotrigine and oxcarbazepine compared with lamotrigine alone or oxcarbazepine alone.

Perampanel

In a pooled analysis of data from 3 placebo-controlled clinical trials investigating adjunctive perampanel in patients with partial-onset and PGTC seizures, the highest perampanel dose evaluated (12 mg/day) increased lamotrigine clearance by <10%. An effect of this magnitude is not considered to be clinically relevant.

Phenobarbital, Primidone

The addition of phenobarbital or primidone decreases lamotrigine steady-state concentrations by approximately 40%.

Phenytoin

Lamotrigine has no appreciable effect on steady-state phenytoin plasma concentrations in patients with epilepsy. The addition of phenytoin decreases lamotrigine steady-state concentrations by approximately 40%.

Pregabalin

Steady-state trough plasma concentrations of lamotrigine were not affected by concomitant pregabalin (200 mg 3 times daily) administration. There are no pharmacokinetic interactions between lamotrigine and pregabalin.

Rifampin

In 10 male volunteers, rifampin (600 mg/day for 5 days) significantly increased the apparent clearance of a single 25-mg dose of lamotrigine by approximately 2-fold (AUC decreased by approximately 40%).

Risperidone

In a 14 healthy volunteers study, multiple oral doses of lamotrigine 400 mg daily had no clinically significant effect on the single-dose pharmacokinetics of risperidone 2 mg and its active metabolite 9-OH risperidone. Following the coadministration of risperidone 2 mg with lamotrigine, 12 of the 14 volunteers reported somnolence compared with 1 out of 20 when risperidone was given alone, and none when lamotrigine was administered alone.

Topiramate

Topiramate resulted in no change in plasma concentrations of lamotrigine. Administration of lamotrigine resulted in a 15% increase in topiramate concentrations.

Valproate

When lamotrigine was administered to healthy volunteers (n = 18) receiving valproate, the trough steady-state valproate plasma concentrations decreased by an average of 25% over a 3-week period, and then stabilized. However, adding lamotrigine to the existing therapy did not cause a change in valproate plasma concentrations in either adult or pediatric patients in controlled clinical trials.

The addition of valproate increased lamotrigine steady-state concentrations in normal volunteers by slightly more than 2-fold. In 1 trial, maximal inhibition of lamotrigine clearance was reached at valproate doses between 250 and 500 mg/day and did not increase as the valproate dose was further increased.

Zonisamide

In a study in 18 patients with epilepsy, coadministration of zonisamide (200 to 400 mg/day) with lamotrigine (150 to 500 mg/day for 35 days) had no significant effect on the pharmacokinetics of lamotrigine.

Known Inducers or Inhibitors of Glucuronidation

Drugs other than those listed above have not been systematically evaluated in combination with lamotrigine. Since lamotrigine is metabolized predominately by glucuronic acid conjugation, drugs that are known to induce or inhibit glucuronidation may affect the apparent clearance of lamotrigine, and doses of LAMICTAL XR may require adjustment based on clinical response.

Other

In vitro assessment of the inhibitory effect of lamotrigine at OCT2 demonstrate that lamotrigine, but not the N(2)-glucuronide metabolite, is an inhibitor of OCT2 at potentially clinically relevant concentrations, with IC50 value of 53.8 µM [see Drug Interactions (7)].

Results of in vitro experiments suggest that clearance of lamotrigine is unlikely to be reduced by concomitant administration of amitriptyline, clonazepam, clozapine, fluoxetine, haloperidol, lorazepam, phenelzine, sertraline, or trazodone.

Results of in vitro experiments suggest that lamotrigine does not reduce the clearance of drugs eliminated predominantly by CYP2D6.

Specific Populations

Patients with Renal Impairment: Twelve volunteers with chronic renal failure (mean creatinine clearance: 13 mL/min, range: 6 to 23) and another 6 individuals undergoing hemodialysis were each given a single 100-mg dose of immediate-release lamotrigine. The mean plasma half-lives determined in the study were 42.9 hours (chronic renal failure), 13.0 hours (during hemodialysis), and 57.4 hours (between hemodialysis) compared with 26.2 hours in healthy volunteers. On average, approximately 20% (range: 5.6 to 35.1) of the amount of lamotrigine present in the body was eliminated by hemodialysis during a 4-hour session [see Dosage and Administration (2.1)].

Patients with Hepatic Impairment: The pharmacokinetics of lamotrigine following a single 100-mg dose of immediate-release lamotrigine were evaluated in 24 subjects with mild, moderate, and severe hepatic impairment (Child-Pugh classification system) and compared with 12 subjects without hepatic impairment. The subjects with severe hepatic impairment were without ascites (n = 2) or with ascites (n = 5). The mean apparent clearances of lamotrigine in subjects with mild (n = 12), moderate (n = 5), severe without ascites (n = 2), and severe with ascites (n = 5) liver impairment were 0.30 ± 0.09, 0.24 ± 0.1, 0.21 ± 0.04, and 0.15 ± 0.09 mL/min/kg, respectively, as compared with 0.37 ± 0.1 mL/min/kg in the healthy controls. Mean half-lives of lamotrigine in subjects with mild, moderate, severe without ascites, and severe with ascites hepatic impairment were 46 ± 20, 72 ± 44, 67 ± 11, and 100 ± 48 hours, respectively, as compared with 33 ± 7 hours in healthy controls [see Dosage and Administration (2.1)].

Geriatric Patients: The pharmacokinetics of lamotrigine following a single 150-mg dose of immediate-release lamotrigine were evaluated in 12 elderly volunteers between the ages of 65 and 76 years (mean creatinine clearance: 61 mL/min, range: 33 to 108 mL/min). The mean half-life of lamotrigine in these subjects was 31.2 hours (range: 24.5 to 43.4 hours), and the mean clearance was 0.40 mL/min/kg (range: 0.26 to 0.48 mL/min/kg).

Male and Female Patients: The clearance of lamotrigine is not affected by gender. However, during dose escalation of immediate-release lamotrigine in 1 clinical trial in patients with epilepsy on a stable dose of valproate (n = 77), mean trough lamotrigine concentrations unadjusted for weight were 24% to 45% higher (0.3 to 1.7 mcg/mL) in females than in males.

Racial or Ethnic Groups: The apparent oral clearance of lamotrigine was 25% lower in non-Caucasians than Caucasians.

Pediatric Patients: Safety and effectiveness of LAMICTAL XR for use in patients younger than 13 years have not been established.

13 NONCLINICAL TOXICOLOGY

13.1 Carcinogenesis, Mutagenesis, Impairment of Fertility

No evidence of carcinogenicity was seen in mice or rats following oral administration of lamotrigine for up to 2 years at doses up to 30 mg/kg/day and 10 to 15 mg/kg/day, respectively. The highest doses tested are less than the human dose of 400 mg/day on a body surface area (mg/m^2) basis.

Lamotrigine was negative in in vitro gene mutation (Ames and mouse lymphoma tk) assays and in clastogenicity (in vitro human lymphocyte and in vivo rat bone marrow) assays.

No evidence of impaired fertility was detected in rats given oral doses of lamotrigine up to 20 mg/kg/day. The highest dose tested is less than the human dose of 400 mg/day on a mg/m^2 basis.

14 CLINICAL STUDIES

14.1 Adjunctive Therapy for Primary Generalized Tonic-Clonic Seizures

The effectiveness of LAMICTAL XR as adjunctive therapy in subjects with PGTC seizures was established in a 19-week, international, multicenter, double-blind, randomized, placebo-controlled trial in 143 patients aged 13 years and older (n = 70 on LAMICTAL XR, n = 73 on placebo). Patients with at least 3 PGTC seizures during an 8-week baseline phase were randomized to 19 weeks of treatment with LAMICTAL XR or placebo added to their current AED regimen of up to 2 drugs. Patients were dosed on a fixed-dose regimen, with target doses ranging from 200 to 500 mg/day of LAMICTAL XR based on concomitant AEDs (target dose = 200 mg for valproate, 300 mg for AEDs not altering plasma lamotrigine levels, and 500 mg for enzyme-inducing AEDs).

The primary efficacy endpoint was percent change from baseline in PGTC seizure frequency during the double-blind treatment phase. For the intent-to-treat population, the median percent reduction in PGTC seizure frequency was 75% in patients treated with LAMICTAL XR and 32% in patients treated with placebo, a difference that was statistically significant, defined as a 2-sided P value <0.05.

Figure 1 presents the percentage of patients (X-axis) with a percent reduction in PGTC seizure frequency (responder rate) from baseline through the entire treatment period at least as great as that represented on the Y-axis. A positive value on the Y-axis indicates an improvement from baseline (i.e., a decrease in seizure frequency), while a negative value indicates a worsening from baseline (i.e., an increase in seizure frequency). Thus, in a display of this type, a curve for an effective treatment is shifted to the left of the curve for placebo. The proportion of patients achieving any particular level of reduction in PGTC seizure frequency was consistently higher for the group treated with LAMICTAL XR compared with the placebo group. For example, 70% of patients randomized to LAMICTAL XR experienced a 50% or greater reduction in PGTC seizure frequency, compared with 32% of patients randomized to placebo. Patients with an increase in seizure frequency >100% are represented on the Y-axis as ≥-100%.

Figure 1. Proportion of Patients by Responder Rate for LAMICTAL XR and Placebo Group (Primary Generalized Tonic-Clonic Seizures Study)

14.2 Adjunctive Therapy for Partial-Onset Seizures

The effectiveness of immediate-release lamotrigine as adjunctive therapy was initially established in 3 pivotal, multicenter, placebo-controlled, double-blind clinical trials in 355 adults with refractory partial-onset seizures.

The effectiveness of LAMICTAL XR as adjunctive therapy in partial-onset seizures, with or without secondary generalization, was established in a 19-week, multicenter, double-blind, placebo-controlled trial in 236 patients aged 13 years and older (approximately 93% of patients were aged 16 to 65 years). Approximately 36% were from the U.S. and approximately 64% were from other countries including Argentina, Brazil, Chile, Germany, India, Korea, Russian Federation, and Ukraine. Patients with at least 8 partial-onset seizures during an 8-week prospective baseline phase (or 4-week prospective baseline coupled with a 4-week historical baseline documented with seizure diary data) were randomized to treatment with LAMICTAL XR (n = 116) or placebo (n = 120) added to their current regimen of 1 or 2 AEDs. Approximately half of the patients were taking 2 concomitant AEDs at baseline. Target doses ranged from 200 to 500 mg/day of LAMICTAL XR based on concomitant AED (target dose = 200 mg for valproate, 300 mg for AEDs not altering plasma lamotrigine, and 500 mg for enzyme-inducing AEDs). The median partial seizure frequency per week at baseline was 2.3 for LAMICTAL XR and 2.1 for placebo.

The primary endpoint was the median percent change from baseline in partial-onset seizure frequency during the entire double-blind treatment phase. The median percent reductions in weekly partial-onset seizures were 47% in patients treated with LAMICTAL XR and 25% on placebo, a difference that was statistically significant, defined as a 2-sided P value ≤0.05.

Figure 2 presents the percentage of patients (X-axis) with a percent reduction in partial-onset seizure frequency (responder rate) from baseline through the entire treatment period at least as great as that represented on the Y-axis. The proportion of patients achieving any particular level of reduction in partial-onset seizure frequency was consistently higher for the group treated with LAMICTAL XR compared with the placebo group. For example, 44% of patients randomized to LAMICTAL XR experienced a 50% or greater reduction in partial-onset seizure frequency compared with 21% of patients randomized to placebo.

Figure 2. Proportion of Patients by Responder Rate for LAMICTAL XR and Placebo Group (Partial-Onset Seizure Study)

14.3 Conversion to Monotherapy for Partial-Onset Seizures

The effectiveness of LAMICTAL XR as monotherapy for partial-onset seizures was established in a historical control trial in 223 adults with partial-onset seizures. The historical control methodology is described in a publication by French, et al. [see References (15)]. Briefly, in this study, patients were randomized to ultimately receive either LAMICTAL XR 300 or 250 mg once a day, and their responses were compared with those of a historical control group. The historical control consisted of a pooled analysis of the control groups from 8 studies of similar design, which utilized a subtherapeutic dose of an AED as a comparator. Statistical superiority to the historical control was considered to be demonstrated if the upper 95% confidence interval for the proportion of patients meeting escape criteria in patients receiving LAMICTAL XR remained below the lower 95% prediction interval of 65.3% derived from the historical control data.

In this study, patients aged 13 years and older experienced at least 4 partial-onset seizures during an 8-week baseline period with at least 1 seizure occurring during each of 2 consecutive 4-week periods while receiving valproate or a non–enzyme-inducing AED. LAMICTAL XR was added to either valproate or a non–enzyme-inducing AED over a 6- to 7-week period followed by the gradual withdrawal of the background AED. Patients were then continued on monotherapy with LAMICTAL XR for 12 weeks. The escape criteria were 1 or more of the following: (1) doubling of average monthly seizure count during any 28 consecutive days, (2) doubling of highest consecutive 2-day seizure frequency during the entire treatment phase, (3) emergence of a new seizure type compared with baseline (4) clinically significant prolongation of generalized tonic-clonic seizures or worsening of seizure considered by the investigator to require intervention. These criteria were similar to those in the 8 controlled trials from which the historical control group was constituted.

The upper 95% confidence limits of the proportion of subjects meeting escape criteria (40.2% at 300 mg/day and 44.5% at 250 mg/day) were below the threshold of 65.3% derived from the historical control data.

Although the study population was not fully comparable with the historical control population and the study was not fully blinded, numerous sensitivity analyses supported the primary results. Efficacy was further supported by the established effectiveness of the immediate-release formulation as monotherapy.

15 REFERENCES

1. French JA, Wang S, Warnock B, Temkin N. Historical control monotherapy design in the treatment of epilepsy. Epilepsia. 2010; 51(10):1936-1943.

16 HOW SUPPLIED/STORAGE AND HANDLING

LAMICTAL XR (lamotrigine) extended-release tablets

25-mg, yellow with a white center, round, biconvex, film-coated tablets printed on one face in black ink with “LAMICTAL” and “XR 25”, unit-of-use bottles of 30 with orange caps (NDC 0173-0754-00).

50-mg, green with a white center, round, biconvex, film-coated tablets printed on one face in black ink with “LAMICTAL” and “XR 50”, unit-of-use bottles of 30 with orange caps (NDC 0173-0755-00).

100-mg, orange with a white center, round, biconvex, film-coated tablets printed on one face in black ink with “LAMICTAL” and “XR 100”, unit-of-use bottles of 30 with orange caps (NDC 0173-0756-00).

200-mg, blue with a white center, round, biconvex, film-coated tablets printed on one face in black ink with “LAMICTAL” and “XR 200”, unit-of-use bottles of 30 with orange caps (NDC 0173-0757-00).

250-mg, purple with a white center, caplet-shaped, film-coated tablets printed on one face in black ink with “LAMICTAL” and “XR 250”, unit-of-use bottles of 30 with orange caps (NDC 0173-0781-00).

300-mg, gray with a white center, caplet-shaped, film-coated tablets printed on one face in black ink with “LAMICTAL” and “XR 300”, unit-of-use bottles of 30 with orange caps (NDC 0173-0761-00).

LAMICTAL XR (lamotrigine) Patient Titration Kit for Patients Taking Valproate (Blue XR Kit)

25-mg, yellow with a white center, round, biconvex, film-coated tablets printed on one face in black ink with “LAMICTAL” and “XR 25” and 50 mg, green with a white center, round, biconvex, film-coated tablets printed on one face in black ink with “LAMICTAL” and “XR 50”; blister pack of 21/25-mg tablets and 7/50-mg tablets (NDC 0173-0758-00).

LAMICTAL XR (lamotrigine) Patient Titration Kit for Patients Taking Carbamazepine, Phenytoin, Phenobarbital, or Primidone, and Not Taking Valproate (Green XR Kit)

50-mg, green with a white center, round, biconvex, film-coated tablets printed on one face in black ink with “LAMICTAL” and “XR 50”; 100 mg, orange with a white center, round, biconvex, film-coated tablets printed on one face in black ink with “LAMICTAL” and “XR 100”; and 200 mg, blue with a white center, round, biconvex, film-coated tablets printed on one face in black ink with “LAMICTAL” and “XR 200”; blister pack of 14/50-mg tablets, 14/100-mg tablets, and 7/200-mg tablets (NDC 0173-0759-00).

LAMICTAL XR (lamotrigine) Patient Titration Kit for Patients Not Taking Carbamazepine, Phenytoin, Phenobarbital, Primidone, or Valproate (Orange XR Kit)

25-mg, yellow with a white center, round, biconvex, film-coated tablets printed on one face in black ink with “LAMICTAL” and “XR 25”; 50 mg, green with a white center, round, biconvex, film-coated tablets printed on one face in black ink with “LAMICTAL” and “XR 50”; and 100 mg, orange with a white center, round, biconvex, film-coated tablets printed on one face in black ink with “LAMICTAL” and “XR 100”; blister pack of 14/25-mg tablets, 14/50-mg tablets, and 7/100-mg tablets (NDC 0173-0760-00).

Storage

Store at 25°C (77°F); excursions permitted to 15°C to 30°C (59°F to 86°F) [see USP Controlled Room Temperature].

17 PATIENT COUNSELING INFORMATION

Advise the patient to read the FDA-approved patient labeling (Medication Guide).

Rash

Prior to initiation of treatment with LAMICTAL XR, inform patients that a rash or other signs or symptoms of hypersensitivity (e.g., fever, lymphadenopathy) may herald a serious medical event and instruct them to report any such occurrence to their healthcare providers immediately.

Hemophagocytic Lymphohistiocytosis

Prior to initiation of treatment with LAMICTAL XR, inform patients that excessive immune activation may occur with LAMICTAL XR and that they should report signs or symptoms such as fever, rash, or lymphadenopathy to a healthcare provider immediately.

Multiorgan Hypersensitivity Reactions, Blood Dyscrasias, and Organ Failure

Inform patients that multiorgan hypersensitivity reactions and acute multiorgan failure may occur with LAMICTAL XR. Isolated organ failure or isolated blood dyscrasias without evidence of multiorgan hypersensitivity may also occur. Instruct patients to contact their healthcare providers immediately if they experience any signs or symptoms of these conditions [see Warnings and Precautions (5.3, 5.5)].

Cardiac Rhythm and Conduction Abnormalities

Inform patients that, due to its mechanism of action, LAMICTAL XR could lead to irregular or slowed heart rhythm. This risk is increased in patients with underlying cardiac disease or heart conduction problems or who are taking other medications that affect heart conduction. Patients should be made aware of and report cardiac signs or symptoms to their healthcare provider right away. Patients who develop syncope should lie down with raised legs and contact their healthcare provider [see Warnings and Precautions (5.4)].

Suicidal Thinking and Behavior

Inform patients, their caregivers, and families that AEDs, including LAMICTAL XR, may increase the risk of suicidal thoughts and behavior. Instruct them to be alert for the emergence or worsening of symptoms of depression, any unusual changes in mood or behavior, or the emergence of suicidal thoughts or behavior or thoughts about self-harm. Instruct them to immediately report behaviors of concern to their healthcare providers.

Worsening of Seizures

Instruct patients to notify their healthcare providers if worsening of seizure control occurs.

Central Nervous System Adverse Effects

Inform patients that LAMICTAL XR may cause dizziness, somnolence, and other symptoms and signs of central nervous system depression. Accordingly, instruct them neither to drive a car nor to operate other complex machinery until they have gained sufficient experience on LAMICTAL XR to gauge whether or not it adversely affects their mental and/or motor performance.

Pregnancy and Nursing

Instruct patients to notify their healthcare providers if they become pregnant or intend to become pregnant during therapy and if they intend to breastfeed or are breastfeeding an infant.

Encourage patients to enroll in the NAAED Pregnancy Registry if they become pregnant. This registry is collecting information about the safety of AEDs during pregnancy. To enroll, patients can call the toll-free number 1-888-233-2334 [see Use in Specific Populations (8.1)].

Inform patients who intend to breastfeed that LAMICTAL XR is present in breast milk and advise them to monitor their child for potential adverse effects of this drug. Discuss the benefits and risks of continuing breastfeeding.

Use of Estrogen-Containing Products, Including Oral Contraceptives

Instruct women to notify their healthcare providers if they plan to start or stop use of oral contraceptives or other female hormonal preparations (including HRT). Starting estrogen-containing products, including oral contraceptives, may significantly decrease lamotrigine plasma levels, and stopping estrogen-containing oral contraceptives (including the pill-free week) may significantly increase lamotrigine plasma levels [see Warnings and Precautions (5.9), Clinical Pharmacology (12.3)]. Also instruct women to promptly notify their healthcare providers if they experience adverse reactions or changes in menstrual pattern (e.g., break-through bleeding) while receiving LAMICTAL XR in combination with these medications.

Discontinuing LAMICTAL XR

Instruct patients to notify their healthcare providers if they stop taking LAMICTAL XR for any reason and not to resume LAMICTAL XR without consulting their healthcare providers.

Aseptic Meningitis

Inform patients that LAMICTAL XR may cause aseptic meningitis. Instruct them to notify their healthcare providers immediately if they develop signs and symptoms of meningitis such as headache, fever, nausea, vomiting, stiff neck, rash, abnormal sensitivity to light, myalgia, chills, confusion, or drowsiness while taking LAMICTAL XR.

Potential Medication Errors

To avoid a medication error of using the wrong drug or formulation, strongly advise patients to visually inspect their tablets to verify that they are LAMICTAL XR each time they fill their prescription [see Dosage Forms and Strengths (3), How Supplied/Storage and Handling (16)]. Refer the patient to the Medication Guide that provides depictions of the LAMICTAL XR extended-release tablets.

LAMICTAL XR is a trademark owned by or licensed to the GSK group of companies. The other brand listed is a trademark owned by or licensed to its owner and is not owned by or licensed to the GSK group of companies. The maker of this brand is not affiliated with and does not endorse the GSK group of companies or its products.

GlaxoSmithKline

Durham, NC 27701

©2025 GSK group of companies or its licensor.

LXR:29PI

MEDICATION GUIDE

LAMICTAL (la-MIK-tal) XR (lamotrigine) extended-release tablets

What is the most important information I should know about LAMICTAL XR?

1. LAMICTAL XR may cause a serious skin rash that may cause you to be hospitalized or even cause death.
  There is no way to tell if a mild rash will become more serious. A serious skin rash can happen at any time during your treatment with LAMICTAL XR, but is more likely to happen within the first 2 to 8 weeks of treatment. Children aged between 2 and 16 years have a higher chance of getting this serious skin rash while taking LAMICTAL XR. LAMICTAL XR is not approved for use in children younger than 13 years.
  The risk of getting a serious skin rash is higher if you:
  1. take LAMICTAL XR while taking valproate [DEPAKENE (valproic acid) or DEPAKOTE (divalproex sodium)].
  2. take a higher starting dose of LAMICTAL XR than your healthcare provider prescribed.
  3. increase your dose of LAMICTAL XR faster than prescribed.
    The risk of serious skin reactions may be associated with a variant in genes called HLA‑B*1502 in people from Asian origin (mainly of Han Chinese and Thai origin). See “Before taking LAMICTAL XR, tell your healthcare provider about all of your health conditions”.
    Call your healthcare provider right away if you have any of the following:

LAMICTAL XR (lamotrigine) extended-release tablets

25 mg, yellow

with white center

Imprinted with

LAMICTAL

XR 25

50 mg, green

with white center

Imprinted with

LAMICTAL

XR 50

100 mg, orange

with white center

Imprinted with

LAMICTAL

XR 100

200 mg, blue

with white center

Imprinted with

LAMICTAL

XR 200

250 mg, purple

with white center

Imprinted with

LAMICTAL

XR 250

300 mg, gray

with white center

Imprinted with

LAMICTAL

XR 300

What is LAMICTAL XR?

- LAMICTAL XR is a prescription medicine used:
  - together with other medicines to treat primary generalized tonic-clonic seizures and partial-onset seizures in people aged 13 years and older.
  - alone when changing from 1 other medicine used to treat partial-onset seizures in people aged 13 years and older.
- It is not known if LAMICTAL XR is safe or effective in children younger than 13 years. Other forms of LAMICTAL can be used in children aged 2 to 12 years.
- It is not known if LAMICTAL XR is safe or effective when used alone as the first treatment of seizures.

Do not take LAMICTAL XR:

- if you have had an allergic reaction to lamotrigine or to any of the inactive ingredients in LAMICTAL XR. See the end of this leaflet for a complete list of ingredients in LAMICTAL XR.

Before taking LAMICTAL XR, tell your healthcare provider about all of your health conditions, including if you:

- have had a rash or allergic reaction to another antiseizure medicine.
- are of Asian origin. have had HLA testing before, and know you are carrying the genetic variant, HLA‑B*1502.
- have or have had depression, mood problems, or suicidal thoughts or behavior.
- have a history of heart problems or irregular heart beats or any of your family members have any heart problem, including genetic abnormalities.
- have had aseptic meningitis after taking LAMICTAL (lamotrigine) or LAMICTAL XR.
- are taking estrogen-containing products, including oral contraceptives (birth control pills) or other female hormonal medicines (such as hormone replacement therapy). Do not start or stop taking birth control pills or other female hormonal medicine until you have talked with your healthcare provider. Tell your healthcare provider if you have any changes in your menstrual pattern such as breakthrough bleeding. Stopping these medicines while you are taking LAMICTAL XR may cause side effects (such as dizziness, lack of coordination, or double vision). Starting these medicines may lessen how well LAMICTAL XR works.
- are pregnant or plan to become pregnant. It is not known if LAMICTAL XR may harm your unborn baby. If you become pregnant while taking LAMICTAL XR, talk to your healthcare provider about registering with the North American Antiepileptic Drug Pregnancy Registry. You can enroll in this registry by calling 1-888-233-2334. The purpose of this registry is to collect information about the safety of AEDs during pregnancy.
- are breastfeeding. LAMICTAL XR passes into breast milk and may cause side effects in a breastfed baby. If you breastfeed while taking LAMICTAL XR, watch your baby closely for trouble breathing, episodes of temporarily stopping breathing, sleepiness, or poor sucking. Call your baby’s healthcare provider right away if you see any of these problems. Talk to your healthcare provider about the best way to feed your baby if you take LAMICTAL XR.

Tell your healthcare provider about all the medicines you take, including prescription and over-the-counter medicines, vitamins, and herbal supplements. LAMICTAL XR and certain other medicines may interact with each other. This may cause serious side effects.

Know the medicines you take. Keep a list of them to show your healthcare provider and pharmacist when you get a new medicine.

How should I take LAMICTAL XR?

- Take LAMICTAL XR exactly as prescribed.
- Your healthcare provider may change your dose. Do not change your dose without talking to your healthcare provider.
- Do not stop taking LAMICTAL XR without talking to your healthcare provider. Stopping LAMICTAL XR suddenly may cause serious problems. For example, if you have epilepsy and you stop taking LAMICTAL XR suddenly, you may have seizures that do not stop. Talk with your healthcare provider about how to stop LAMICTAL XR slowly.
- If you miss a dose of LAMICTAL XR, take it as soon as you remember. If it is almost time for your next dose, just skip the missed dose. Take the next dose at your regular time. Do not take 2 doses at the same time.
- If you take too much LAMICTAL XR, call your healthcare provider or your local Poison Control Center or go to the nearest hospital emergency room right away.
- You may not feel the full effect of LAMICTAL XR for several weeks.
- If you have epilepsy, tell your healthcare provider if your seizures get worse or if you have any new types of seizures.
- LAMICTAL XR can be taken with or without food.
- Do not chew, crush, or divide LAMICTAL XR.
- Swallow LAMICTAL XR tablets whole.
- If you have trouble swallowing LAMICTAL XR tablets, tell your healthcare provider because there may be another form of LAMICTAL you can take.
- If you receive LAMICTAL XR in a blister pack, examine the blister pack before use. Do not use if blisters are torn, broken, or missing.

What should I avoid while taking LAMICTAL XR?

Do not drive, operate machinery, or do other dangerous activities until you know how LAMICTAL XR affects you.

What are the possible side effects of LAMICTAL XR?

LAMICTAL XR can cause serious side effects.

See “What is the most important information I should know about LAMICTAL XR?”

Common side effects of LAMICTAL XR include:

- dizziness
- tremor
- double vision
- nausea

- vomiting
- trouble with balance and coordination
- anxiety

Other common side effects that have been reported with another form of LAMICTAL include headache, sleepiness, blurred vision, runny nose, and rash.

These are not all the possible side effects of LAMICTAL XR.

Call your doctor for medical advice about side effects. You may report side effects to FDA at 1-800-FDA-1088.

How should I store LAMICTAL XR?

- Store LAMICTAL XR at room temperature between 59°F and 86°F (15°C and 30°C).

Keep LAMICTAL XR and all medicines out of the reach of children.

General information about the safe and effective use of LAMICTAL XR

Medicines are sometimes prescribed for purposes other than those listed in a Medication Guide. Do not use LAMICTAL XR for a condition for which it was not prescribed. Do not give LAMICTAL XR to other people, even if they have the same symptoms that you have. It may harm them.

If you take a urine drug screening test, LAMICTAL XR may make the test result positive for another drug. If you require a urine drug screening test, tell the healthcare professional administering the test that you are taking LAMICTAL XR.

You can ask your healthcare provider or pharmacist for information about LAMICTAL XR that is written for health professionals.

What are the ingredients in LAMICTAL XR?

Active ingredient: lamotrigine.

Inactive ingredients: glycerol monostearate, hypromellose, lactose monohydrate, magnesium stearate, methacrylic acid copolymer dispersion, polyethylene glycol 400, polysorbate 80, silicon dioxide (25- and 50-mg tablets only), titanium dioxide, triethyl citrate, carmine (250-mg tablet only), iron oxide black (50-, 250-, and 300-mg tablets only), iron oxide yellow (25-, 50-, and 100-mg tablets only), iron oxide red (100-mg tablet only), FD&C Blue No. 2 Aluminum Lake (200- and 250-mg tablets only). Tablets are printed with edible black ink.

For more information about LAMICTAL XR, call 1-888-825-5249.

LAMICTAL XR is a trademark owned by or licensed to the GSK group of companies. The other brands listed are trademarks owned by or licensed to their respective owners and are not owned by or licensed to the GSK group of companies. The makers of these brands are not affiliated with and do not endorse the GSK group of companies or its products.

Distributed by GlaxoSmithKline, Durham, NC 27701

©2025 GSK group of companies or its licensor.

LXR:22MG

This Medication Guide has been approved by the U.S. Food and Drug Administration Revised: October 2025

PACKAGE LABEL

PRINCIPAL DISPLAY PANEL

NDC 0173-0754-00

LAMICTAL XR

(LAMOTRIGINE)

EXTENDED-RELEASE TABLETS

25 mg

Once A Day • LAMICTAL XR • Once a Day • LAMICTAL XR

RX only

CAUTION: Verify Product Dispensed

30 Tablets

Dispense the accompanying Medication Guide to each patient.

See prescribing information for dosage information.

Do not accept if safety seal under cap is missing or broken.

Store at 25oC (77oF); excursions permitted to 15oC to 30oC (59oF to 86oF) [see USP Controlled Room Temperature].

GlaxoSmithKline

Durham, NC 27701

Made in India

Trademark owned or licensed by GSK.

©2023 GSK group of companies or its licensor.

Rev. 5/23

A087133 (62000000087133)

PACKAGE LABEL

PRINCIPAL DISPLAY PANEL

NDC 0173-0755-00

LAMICTAL XR

(LAMOTRIGINE)

EXTENDED-RELEASE TABLETS

50 mg

Once A Day • LAMICTAL XR • Once a Day • LAMICTAL XR

Rx only

CAUTION: Verify Product Dispensed

30 tablets

Dispense the accompanying Medication Guide to each patient.

See prescribing information for dosage information.

Do not accept if safety seal under cap is missing or broken.

Store at 25oC (77oF); excursions permitted to 15oC to 30oC (59oF to 86oF) [see USP Controlled Room Temperature].

GlaxoSmithKline

Durham, NC 27701

Made in India

Trademark owned or licensed by GSK.

©2023 GSK group of companies or its licensor.

Rev. 5/23

A087136 (62000000087136)

PACKAGE LABEL

PRINCIPAL DISPLAY PANEL

NDC 0173-0756-00

LAMICTAL XR

(LAMOTRIGINE)

EXTENDED-RELEASE TABLETS

100 mg

Once A Day • LAMICTAL XR • Once a Day • LAMICTAL XR

Rx only

CAUTION: Verify Product Dispensed

30 tablets

Dispense the accompanying Medication Guide to each patient.

See prescribing information for dosage information.

Do not accept if safety seal under cap is missing or broken.

Store at 25oC (77oF); excursions permitted to 15oC to 30oC (59oF to 86oF) [see USP Controlled Room Temperature].

GlaxoSmithKline

Durham, NC 27701

Made in India

Trademark owned or licensed by GSK.

©2023 GSK group of companies or its licensor.

Rev. 5/23

A087132 (62000000087132)

PACKAGE LABEL

PRINCIPAL DISPLAY PANEL

NDC 0173-0757-00

LAMICTAL XR

(LAMOTRIGINE)

EXTENDED-RELEASE TABLETS

200 mg

Once A Day • LAMICTAL XR • Once a Day • LAMICTAL XR

Rx only

CAUTION: Verify Product Dispensed

30 tablets

Dispense the accompanying Medication Guide to each patient.

See prescribing information for dosage information.

Do not accept if safety seal under cap is missing or broken.

Store at 25oC (77oF); excursions permitted to 15oC to 30oC (59oF to 86oF) [see USP Controlled Room Temperature].

GlaxoSmithKline

Durham, NC 27701

Made in India

Trademark owned or licensed by GSK.

©2023 GSK group of companies or its licensor.

Rev. 5/23

A087135 (62000000087135)

PACKAGE LABEL

PRINCIPAL DISPLAY PANEL

NDC 0173-0781-00

LAMICTAL XR

(LAMOTRIGINE)

EXTENDED- RELEASE TABLETS

250 mg

Once A Day • LAMICTAL XR • Once a Day • LAMICTAL XR

Rx only

CAUTION: Verify Product Dispensed

30 tablets

Dispense the accompanying Medication Guide to each patient.

See prescribing information for dosage information.

Do not accept if safety seal under cap is missing or broken.

Store at 25oC (77oF); excursions permitted to 15oC to 30oC (59oF to 86oF) [see USP Controlled Room Temperature].

GlaxoSmithKline

Durham, NC 27701

Made in India

Trademark owned or licensed by GSK.

©2023 GSK group of companies or its licensor.

Rev. 5/23

A087134 (62000000087134)

PACKAGE LABEL

PRINCIPAL DISPLAY PANEL

NDC 0173-0761-00

LAMICTAL XR

(LAMOTRIGINE)

EXTENDED- RELEASE TABLETS

300 mg

Once A Day • LAMICTAL XR • Once a Day • LAMICTAL XR

Rx only

CAUTION: Verify Product Dispensed

30 tablets

Dispense the accompanying Medication Guide to each patient.

See prescribing information for dosage information.

Do not accept if safety seal under cap is missing or broken.

Store at 25oC (77oF); excursions permitted to 15oC to 30oC (59oF to 86oF) [see USP Controlled Room Temperature].

GlaxoSmithKline

Durham, NC 27701

Made in India

Trademark owned or licensed by GSK.

©2023 GSK group of companies or its licensor.

Rev. 5/23

A087131 (62000000087131)

PACKAGE LABEL

PRINCIPAL DISPLAY PANEL

NDC 0173-0758-00

LAMICTALXR

(LAMOTRIGINE)

EXTENDED-RELEASE TABLETS

LAMICTALXR • LAMICTAL XR • LAMICTAL XR • LAMICTAL XR

Rx only

For patients TAKING valproate*

*See prescribing information for other drugs that may affect dosing of LAMICTAL XR.

PATIENT TITRATION KIT:

21 25-mg Tablets

Each tablet contains 25 mg of lamotrigine

7 50-mg Tablets

Each tablet contains 50 mg of lamotrigine

Please check with your physician about proper maintenance dose before week 5.

Weeks | Tablets per day
1 & 2 | Take 1 (25mg) tablet every OTHER day
3 &4 | Take 1 (25mg) tablet ONCE a DAY
5 | Take 1 (50mg) tablet ONCE a DAY

Dispense the accompanying Medication Guide to each patient.

CAUTION: Verify Product Dispensed

Made in India

©2023 GSK group of companies or its licensor

546721-02 Rev. 6/23

PACKAGE LABEL

PRINCIPAL DISPLAY PANEL

NDC 0173-0759-00

LAMICTAL XR

(LAMOTRIGINE)

EXTENDED-RELEASE TABLETS

LAMICTALXR • LAMICTAL XR • LAMICTAL XR • LAMICTAL XR

Rx only

For patients TAKING carbamazepine, phenytoin, phenobarbital, or primidone and NOT TAKING valproate*

*See prescribing information for other drugs that may affect dosing of LAMICTAL XR.

PATIENT TITRATION KIT:

14 50-mg Tablets

Each tablet contains 50 mg of lamotrigine

14 100-mg Tablets

Each tablet contains 100 mg of lamotrigine

7 200-mg Tablets

Each tablet contains 200 mg of lamotrigine

Please check with your physician about proper maintenance dose before week 5.

Weeks | Tablets per day
1 & 2 | Take 1 (50mg) tablet ONCE a DAY
3 &4 | Take 1 (100mg) tablet ONCE a DAY
5 | Take 1 (200mg) tablet ONCE a DAY

Dispense the accompanying Medication Guide to each patient.

CAUTION: Verify Product Dispensed

Made in India

©2023 GSK group of companies or its licensor

546720-02 Rev. 5/23

PACKAGE LABEL

PRINCIPAL DISPLAY PANEL

NDC 0173-0760-00

LAMICTAL XR

(LAMOTRIGINE)

EXTENDED-RELEASE TABLETS

LAMICTALXR • LAMICTAL XR • LAMICTAL XR • LAMICTAL XR

Rx only

For patients NOT TAKING carbamazepine, phenytoin, phenobarbital, primidone, or valproate*

*See prescribing information for other drugs that may affect dosing of LAMICTAL XR.

PATIENT TITRATION KIT:

14 25-mg Tablets

Each tablet contains 25 mg of lamotrigine

14 50-mg Tablets

Each tablet contains 50 mg of lamotrigine

7 100-mg Tablets

Each tablet contains 100 mg of lamotrigine

Please check with your physician about proper maintenance dose before week 5.

Weeks | Tablets per day
1 & 2 | Take 1 (25mg) tablet ONCE a DAY
3 & 4 | Take 1 (50mg) tablet ONCE a DAY
5 | Take 1 (100mg) tablet ONCE a DAY

Dispense the accompanying Medication Guide to each patient.

CAUTION: Verify Product Dispensed

Made in India

©2023 GSK group of companies or its licensor

546722-02 Rev. 5/23